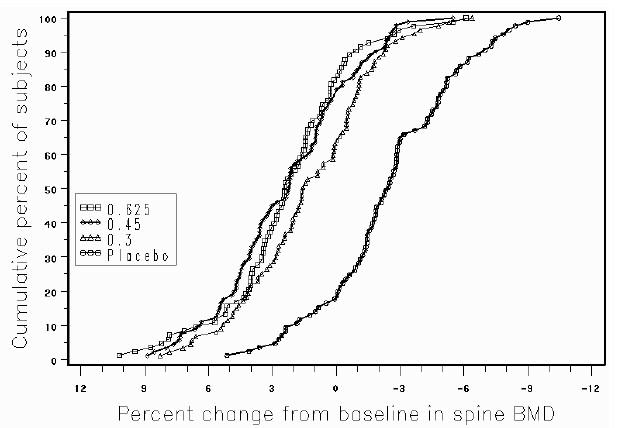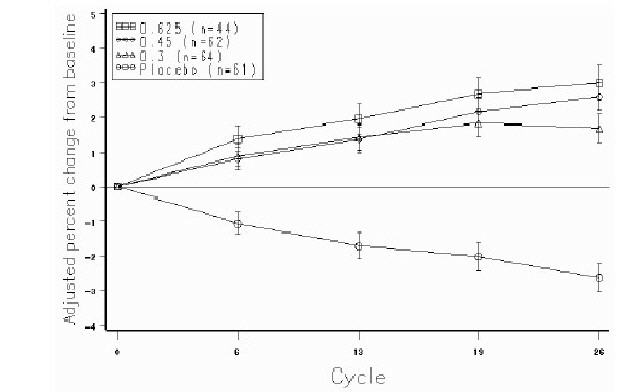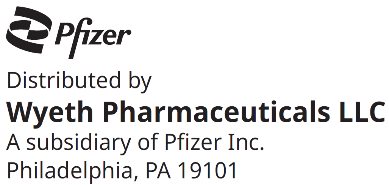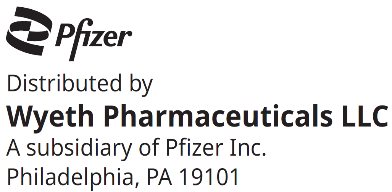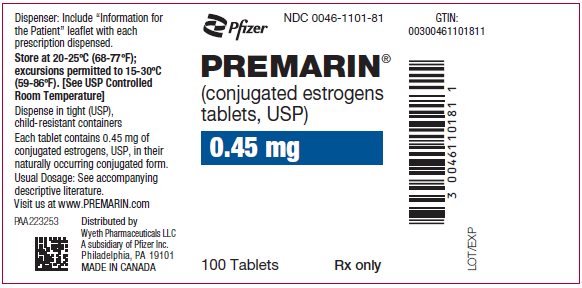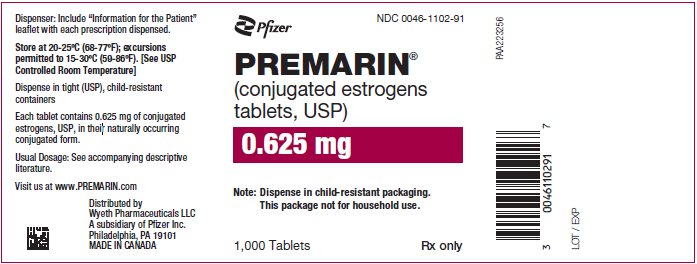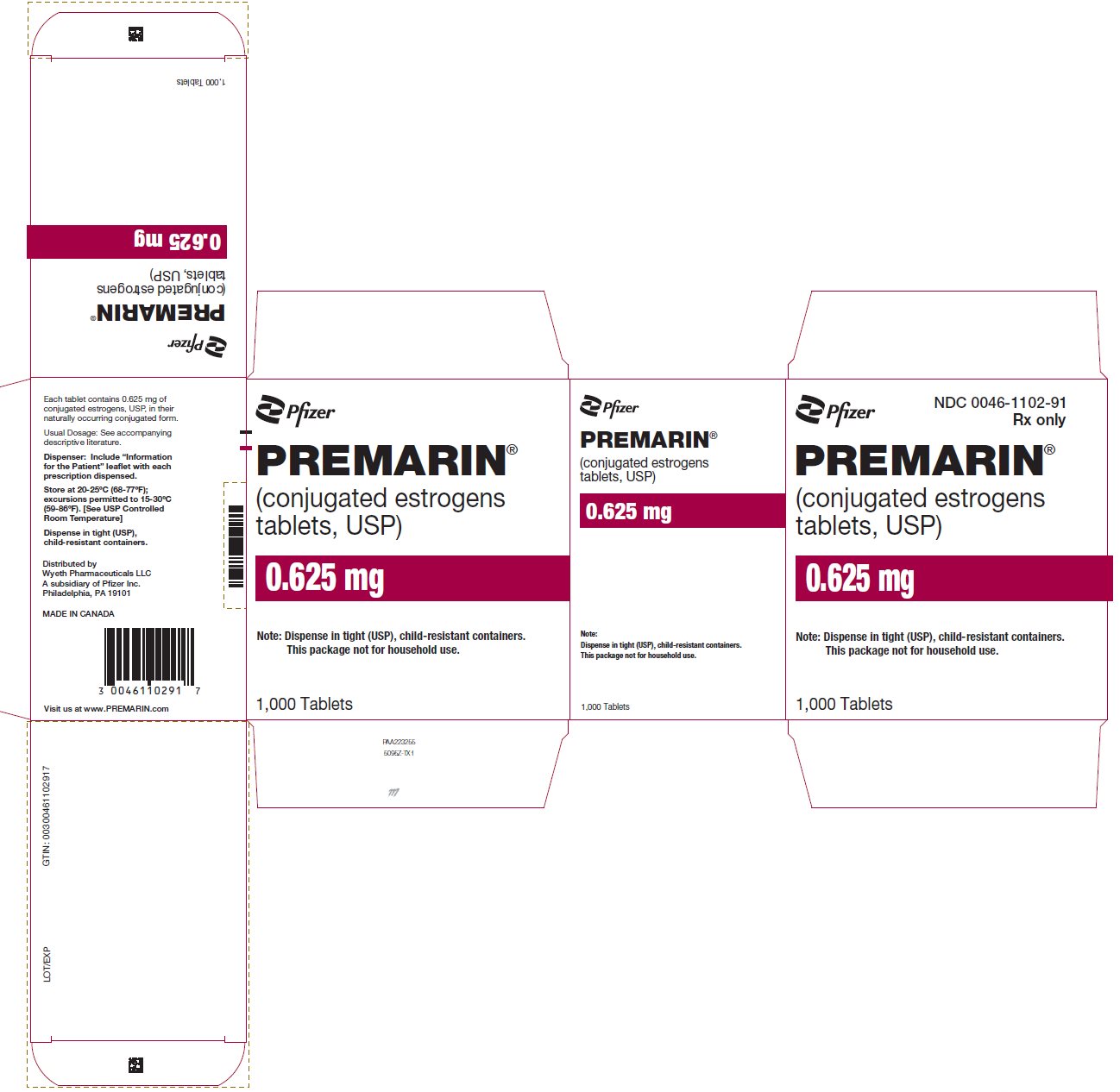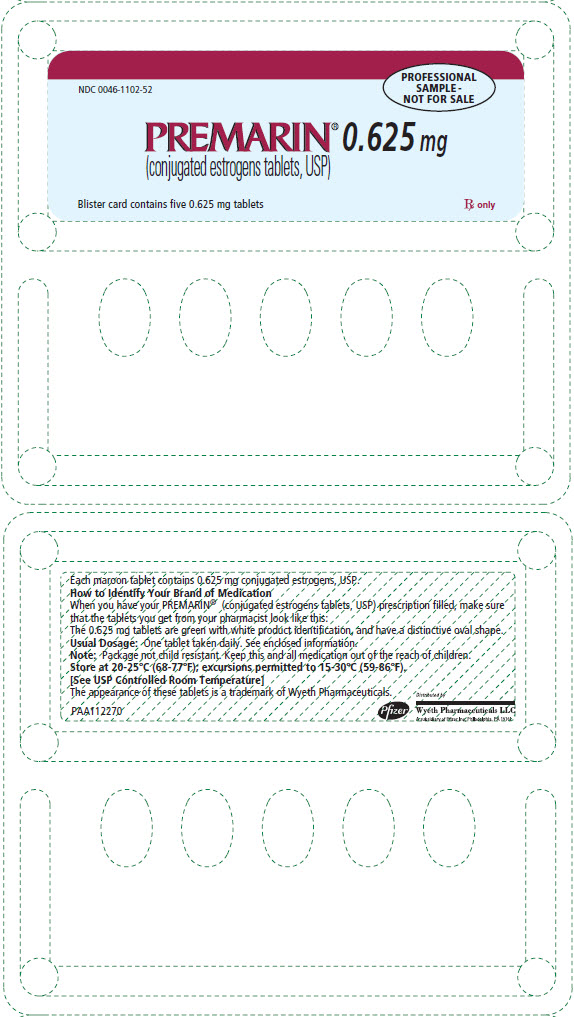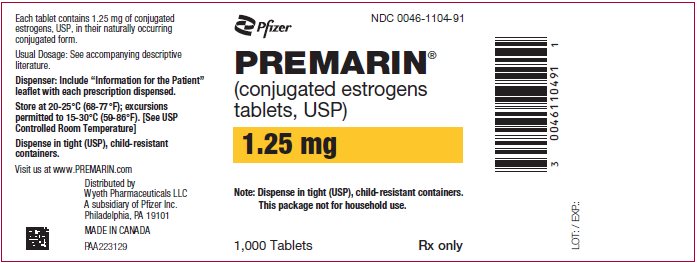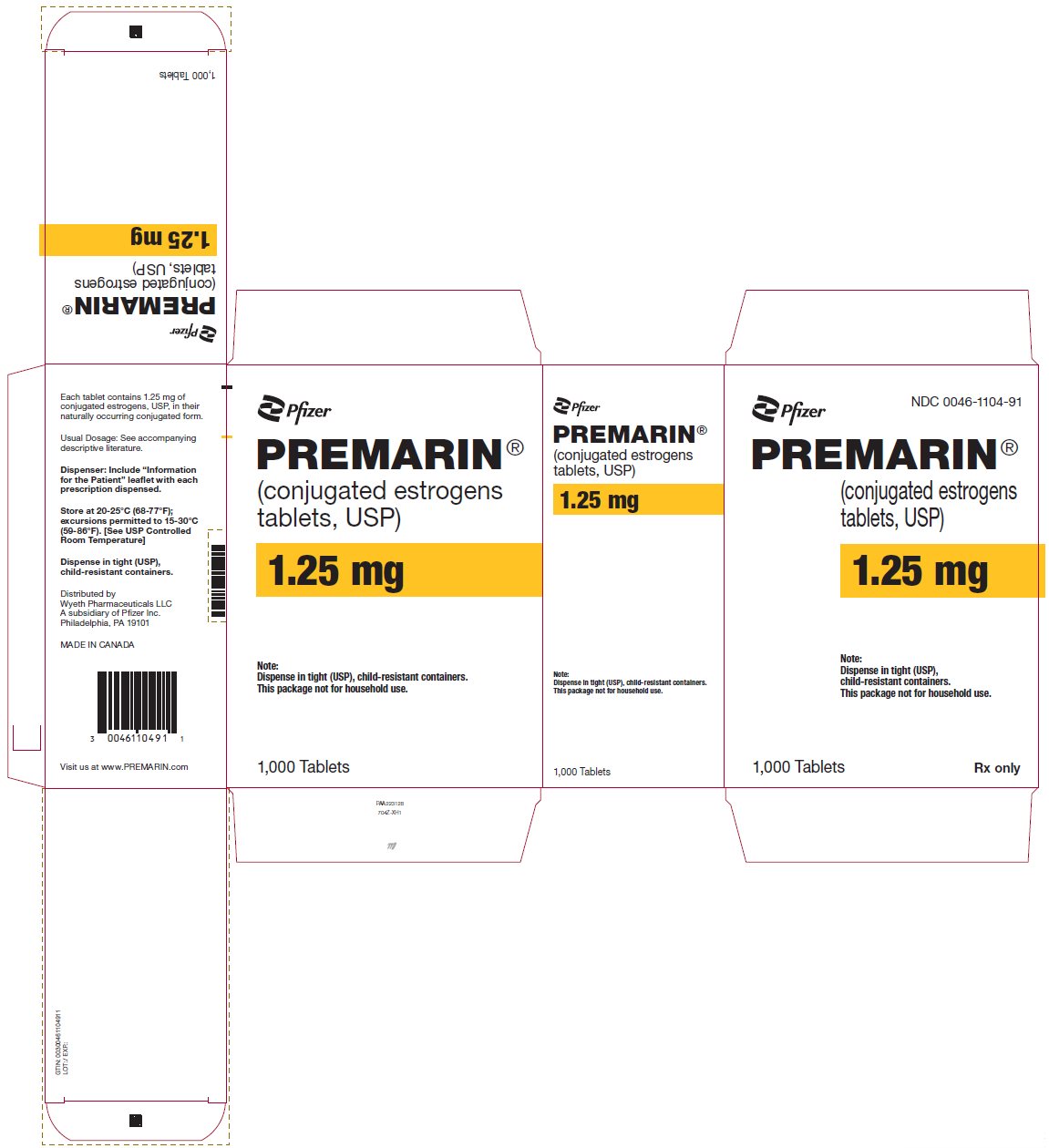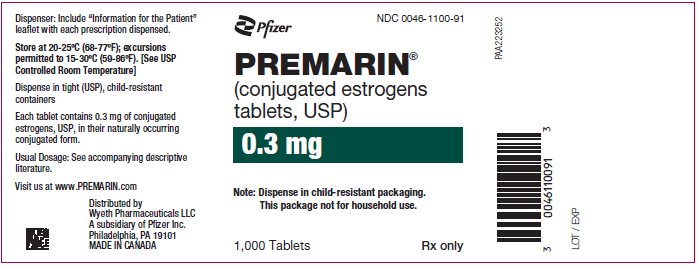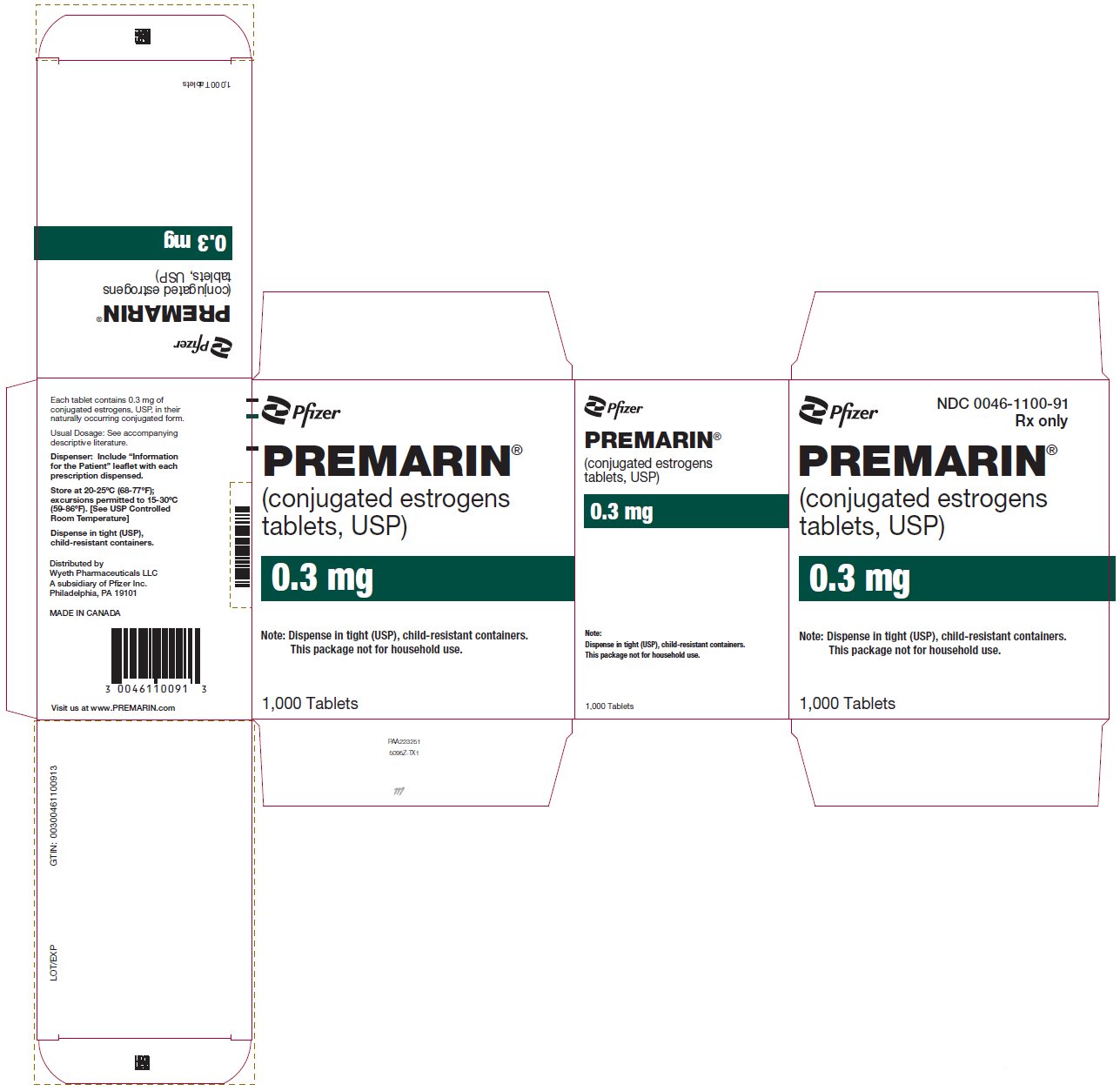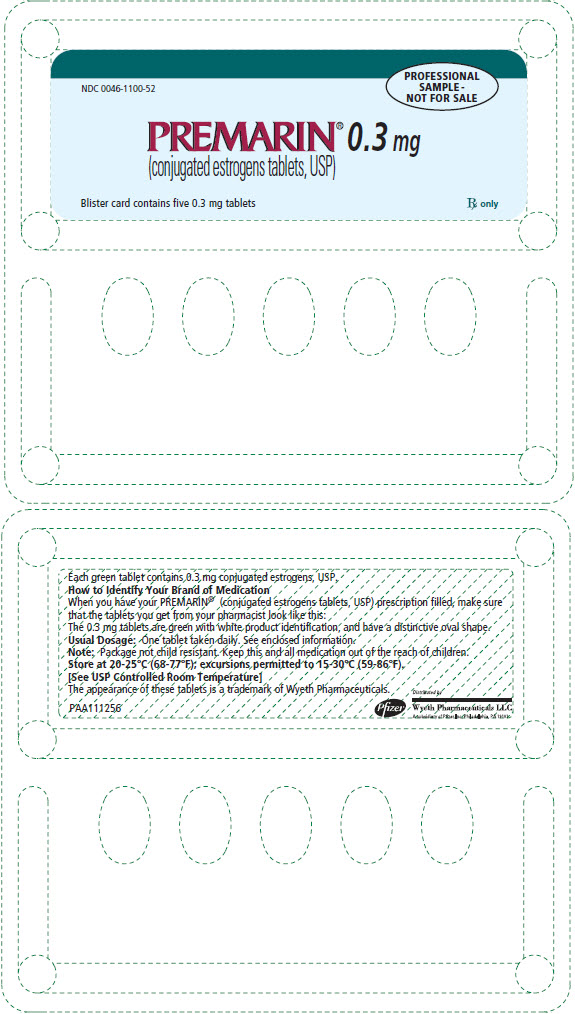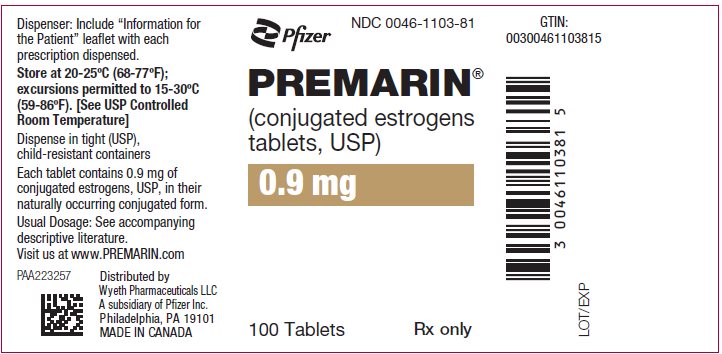 DRUG LABEL: Premarin
NDC: 0046-1101 | Form: TABLET, FILM COATED
Manufacturer: Wyeth Pharmaceuticals LLC, a subsidiary of Pfizer Inc.
Category: prescription | Type: HUMAN PRESCRIPTION DRUG LABEL
Date: 20260220

ACTIVE INGREDIENTS: ESTROGENS, CONJUGATED 0.45 mg/1 1
INACTIVE INGREDIENTS: TRIBASIC CALCIUM PHOSPHATE; HYDROXYPROPYL CELLULOSE (1600000 WAMW); MICROCRYSTALLINE CELLULOSE; POWDERED CELLULOSE; LACTOSE MONOHYDRATE; MAGNESIUM STEARATE; POLYETHYLENE GLYCOL 400; SUCROSE; TITANIUM DIOXIDE; FD&C BLUE NO. 2; CARNAUBA WAX; HYPROMELLOSE 2208 (15000 MPA.S); HYPROMELLOSE 2910 (6 MPA.S); HYPROMELLOSE 2910 (15 MPA.S); HYPROMELLOSE 2910 (3 MPA.S); POLYSORBATE 80

HIGHLIGHTS OF PRESCRIBING INFORMATION

These highlights do not include all the information needed to use PREMARIN safely and effectively. See full prescribing information for PREMARIN.
PREMARIN® (conjugated estrogens) tablets, for oral use
Initial U.S. Approval: 1942

WARNING: ENDOMETRIAL CANCER, CARDIOVASCULAR DISORDERS, BREAST CANCER and PROBABLE DEMENTIA

See full prescribing information for complete boxed warning.

Estrogen-Alone Therapy

- There is an increased risk of endometrial cancer in a woman with a uterus who uses unopposed estrogens (5.2)
- Estrogen-alone therapy should not be used for the prevention of cardiovascular disease or dementia (5.1, 5.3)
- Women's Health Initiative (WHI) estrogen-alone substudy reported increased risks of stroke and deep vein thrombosis (DVT) (5.1)
- The WHI Memory Study (WHIMS) estrogen-alone ancillary study of WHI reported an increased risk of probable dementia in postmenopausal women 65 years of age and older (5.3)

Estrogen Plus Progestin Therapy

- Estrogen plus progestin therapy should not be used for the prevention of cardiovascular disease or dementia (5.1, 5.3)
- The WHI estrogen plus progestin substudy reported increased risks of stroke, DVT, pulmonary embolism (PE), and myocardial infarction (MI) (5.1)
- The WHI estrogen plus progestin substudy reported increased risks of invasive breast cancer (5.2)
- The WHIMS estrogen plus progestin ancillary study of WHI reported an increased risk of probable dementia in postmenopausal women 65 years of age and older (5.3)

1 INDICATIONS AND USAGE

PREMARIN is a mixture of estrogens indicated for:

- Treatment of Moderate to Severe Vasomotor Symptoms due to Menopause (1.1)
- Treatment of Moderate to Severe Vulvar and Vaginal Atrophy due to Menopause (1.2)
- Treatment of Hypoestrogenism due to Hypogonadism, Castration or Primary Ovarian Failure (1.3)
- Treatment of Breast Cancer (for Palliation Only) in Appropriately Selected Women and Men with Metastatic Disease (1.4)
- Treatment of Advanced Androgen-Dependent Carcinoma of the Prostate (for Palliation Only) (1.5)
- Prevention of Postmenopausal Osteoporosis (1.6)

2 DOSAGE AND ADMINISTRATION

- Daily administration of 0.3, 0.45, 0.625, 0.9, and 1.25 mg (2.1, 2.2, 2.3, 2.5, 2.6)
- Cyclic administration of 0.3, 0.625, and 1.25 mg (2.1, 2.2, 2.3)

3 DOSAGE FORMS AND STRENGTHS

Tablets: 0.3, 0.45, 0.625, 0.9, and 1.25 mg (3)

4 CONTRAINDICATIONS

- Undiagnosed abnormal genital bleeding (4)
- Breast cancer or history of breast cancer except in appropriately selected patients being treated for metastatic diseases (4, 5.2)
- Estrogen-dependent neoplasia (4, 5.2)
- Active DVT, PE, or a history of these conditions (4, 5.1)
- Active arterial thromboembolic disease (for example, stroke and MI), or a history of these conditions (4, 5.1)
- Known anaphylactic reaction or angioedema with PREMARIN (5.7, 5.15)
- Hepatic impairment or disease (4, 5.11)
- Protein C, protein S, or antithrombin deficiency, or other known thrombophilic disorders (4)

5 WARNINGS AND PRECAUTIONS

- Estrogens increase the risk of gallbladder disease (5.4)
- Discontinue estrogen if severe hypercalcemia, loss of vision, severe hypertriglyceridemia or cholestatic jaundice occurs (5.5, 5.6, 5.10, 5.11)
- Monitor thyroid function in patients on thyroid replacement therapy (5.12, 5.19)

6 ADVERSE REACTIONS

Most common adverse reactions (≥5%) are: abdominal pain, asthenia, pain, back pain, headache, flatulence, nausea, depression, insomnia, breast pain, endometrial hyperplasia, leucorrhea, vaginal hemorrhage, and vaginitis. (6.1)
To report SUSPECTED ADVERSE REACTIONS, contact Pfizer Inc. at 1-800-438-1985 or FDA at 1-800-FDA-1088 or www.fda.gov/medwatch

7 DRUG INTERACTIONS

Inducers and/or inhibitors of CYP3A4 may affect estrogen drug metabolism (7.1)

8 USE IN SPECIFIC POPULATIONS

- Lactation: Estrogen administration to lactating women has been shown to decrease the quantity and quality of breast milk (8.2)
- Geriatric Use: An increased risk of probable dementia in women over 65 years of age was reported in the Women's Health Initiative Memory ancillary studies of the Women's Health Initiative (5.3, 8.5)

FULL PRESCRIBING INFORMATION

WARNING: ENDOMETRIAL CANCER, CARDIOVASCULAR DISORDERS, BREAST CANCER and PROBABLE DEMENTIA

Estrogen-Alone Therapy

Endometrial Cancer

There is an increased risk of endometrial cancer in a woman with a uterus who uses unopposed estrogens. Adding a progestin to estrogen therapy has been shown to reduce the risk of endometrial hyperplasia, which may be a precursor to endometrial cancer. Adequate diagnostic measures, including directed or random endometrial sampling when indicated, should be undertaken to rule out malignancy in postmenopausal women with undiagnosed persistent or recurring abnormal genital bleeding [see Warnings and Precautions (5.2)].

Cardiovascular Disorders and Probable Dementia

Estrogen-alone therapy should not be used for the prevention of cardiovascular disease or dementia [see Warnings and Precautions (5.1, 5.3), and Clinical Studies (14.5, 14.6)].

The Women's Health Initiative (WHI) estrogen-alone substudy reported increased risks of stroke and deep vein thrombosis (DVT) in postmenopausal women (50 to 79 years of age) during 7.1 years of treatment with daily oral conjugated estrogens (CE) (0.625 mg)‑alone, relative to placebo [see Warnings and Precautions (5.1), and Clinical Studies (14.5)].

The WHI Memory Study (WHIMS) estrogen-alone ancillary study of WHI reported an increased risk of developing probable dementia in postmenopausal women 65 years of age or older during 5.2 years of treatment with daily CE (0.625 mg)-alone, relative to placebo. It is unknown whether this finding applies to younger postmenopausal women [see Warnings and Precautions (5.3), Use in Specific Populations (8.5), and Clinical Studies (14.6)].

In the absence of comparable data, these risks should be assumed to be similar for other doses of CE and other dosage forms of estrogens.

Estrogens with or without progestins should be prescribed at the lowest effective doses and for the shortest duration consistent with treatment goals and risks for the individual woman.

Estrogen Plus Progestin Therapy

Cardiovascular Disorders and Probable Dementia

Estrogen plus progestin therapy should not be used for the prevention of cardiovascular disease or dementia [see Warnings and Precautions (5.1, 5.3), and Clinical Studies (14.5, 14.6)].

The WHI estrogen plus progestin substudy reported increased risks of DVT, pulmonary embolism (PE), stroke and myocardial infarction (MI) in postmenopausal women (50 to 79 years of age) during 5.6 years of treatment with daily oral CE (0.625 mg) combined with medroxyprogesterone acetate (MPA) [2.5 mg], relative to placebo [see Warnings and Precautions (5.1), and Clinical Studies (14.5)].

The WHIMS estrogen plus progestin ancillary study of the WHI, reported an increased risk of developing probable dementia in postmenopausal women 65 years of age or older during 4 years of treatment with daily CE (0.625 mg) combined with MPA (2.5 mg), relative to placebo. It is unknown whether this finding applies to younger postmenopausal women [see Warnings and Precautions (5.3), Use in Specific Populations (8.5), and Clinical Studies (14.6)].

Breast Cancer

The WHI estrogen plus progestin substudy also demonstrated an increased risk of invasive breast cancer [see Warnings and Precautions (5.2), and Clinical Studies (14.5)].

In the absence of comparable data, these risks should be assumed to be similar for other doses of CE and MPA, and other combinations and dosage forms of estrogens and progestins.

Estrogens with or without progestins should be prescribed at the lowest effective doses and for the shortest duration consistent with treatment goals and risks for the individual woman.

1 INDICATIONS AND USAGE

1.2 Treatment of Moderate to Severe Symptoms of Vulvar and Vaginal Atrophy due to Menopause

Limitations of Use

When prescribing solely for the treatment of moderate to severe symptoms of vulvar and vaginal atrophy due to menopause, topical vaginal products should be considered.

1.6 Prevention of Postmenopausal Osteoporosis

Limitations of Use

When prescribing solely for the prevention of postmenopausal osteoporosis, therapy should only be considered for women at significant risk of osteoporosis and non-estrogen medication should be carefully considered.

2 DOSAGE AND ADMINISTRATION

Generally, when estrogen therapy is prescribed for a postmenopausal woman with a uterus, a progestin should be considered to reduce the risk of endometrial cancer [see Boxed Warning].

A woman without a uterus does not need progestin. In some cases, however, hysterectomized women with a history of endometriosis may need a progestin [see Warnings and Precautions (5.2, 5.16)].

Use of estrogen-alone, or in combination with a progestin, should be with the lowest effective dose and for the shortest duration consistent with treatment goals and risks for the individual woman. Postmenopausal women should be re-evaluated periodically as clinically appropriate to determine if treatment is still necessary.

PREMARIN may be taken without regard to meals.

2.1 Treatment of Moderate to Severe Vasomotor Symptoms due to Menopause

Patients should be treated with the lowest effective dose. Generally, women should be started at 0.3 mg PREMARIN daily. Subsequent dosage adjustment may be made based upon the individual patient response. This dose should be periodically reassessed by the healthcare provider.

PREMARIN therapy may be given continuously, with no interruption in therapy, or in cyclical regimens (regimens such as 25 days on drug followed by 5 days off drug), as is medically appropriate on an individual basis.

2.2 Treatment of Moderate to Severe Symptoms of Vulvar and Vaginal Atrophy due to Menopause

Patients should be treated with the lowest effective dose. Generally, women should be started at 0.3 mg PREMARIN daily. Subsequent dosage adjustment may be made based upon the individual patient response. This dose should be periodically reassessed by the healthcare provider.

PREMARIN therapy may be given continuously, with no interruption in therapy, or in cyclical regimens (regimens such as 25 days on drug followed by 5 days off drug), as is medically appropriate on an individual basis.

2.3 Treatment of Hypoestrogenism due to Hypogonadism, Castration, or Primary Ovarian Failure

PREMARIN therapy should be initiated and maintained with the lowest effective dose to achieve clinical goals. Female hypogonadism: 0.3 mg or 0.625 mg daily, administered cyclically (e.g., three weeks on and one week off). Doses are adjusted depending on the severity of symptoms and responsiveness of the endometrium [see Clinical Studies (14.4)].

Female castration or primary ovarian failure: 1.25 mg daily, cyclically. Adjust dosage, upward or downward, according to severity of symptoms and response of the patient. For maintenance, adjust dosage to lowest level that will provide effective control.

2.4 Treatment of Breast Cancer (for Palliation Only) in Appropriately Selected Women and Men with Metastatic Disease

Suggested dosage is 10 mg three times daily, for a period of at least three months.

2.5 Treatment of Advanced Androgen-Dependent Carcinoma of the Prostate (for Palliation Only)

1.25 mg to 2 × 1.25 mg three times daily. The effectiveness of therapy can be judged by phosphatase determinations as well as by symptomatic improvement of the patient.

2.6 Prevention of Postmenopausal Osteoporosis

PREMARIN therapy may be given continuously, with no interruption in therapy, or in cyclical regimens (regimens such as 25 days on drug followed by 5 days off drug), as is medically appropriate on an individual basis.

Patients should be treated with the lowest effective dose. Generally, women should be started at 0.3 mg PREMARIN daily. Subsequent dosage adjustment may be made based upon the individual clinical and bone mineral density responses. This dose should be periodically reassessed by the healthcare provider.

3 DOSAGE FORMS AND STRENGTHS

PREMARIN (conjugated estrogens tablets, USP)

Tablet Strength | Tablet Shape/Color | Imprint
0.3 mg | oval/green | PREMARIN 0.3
0.45 mg | oval/blue | PREMARIN 0.45
0.625 mg | oval/maroon | PREMARIN 0.625
0.9 mg | oval/white | PREMARIN 0.9
1.25 mg | oval/yellow | PREMARIN 1.25

4 CONTRAINDICATIONS

PREMARIN therapy is contraindicated in individuals with any of the following conditions:

- Undiagnosed abnormal genital bleeding [see Warnings and Precautions (5.2)]
- Breast cancer or a history of breast cancer except in appropriately selected patients being treated for metastatic disease [see Warnings and Precautions (5.2)]
- Estrogen-dependent neoplasia [see Warnings and Precautions (5.2)]
- Active DVT, PE, or a history of these conditions [see Warnings and Precautions (5.1)]
- Active arterial thromboembolic disease (for example stroke and MI), or a history of these conditions [see Warnings and Precautions (5.1)]
- Known anaphylactic reaction or angioedema with PREMARIN [see Warnings and Precautions (5.7, 5.15)]
- Hepatic impairment or disease [see Warnings and Precautions (5.11)]
- Protein C, protein S or antithrombin deficiency, or other known thrombophilic disorders.

5 WARNINGS AND PRECAUTIONS

5.1 Cardiovascular Disorders

An increased risk of stroke and DVT has been reported with estrogen-alone therapy. An increased risk of PE, DVT, stroke and MI has been reported with estrogen plus progestin therapy. Should any of these events occur or be suspected, estrogen with or without progestin therapy should be discontinued immediately.

Risk factors for arterial vascular disease (for example, hypertension, diabetes mellitus, tobacco use, hypercholesterolemia, and obesity) and/or venous thromboembolism (VTE) (for example, personal or family history of VTE, obesity, and systemic lupus erythematosus) should be managed appropriately.

Stroke

In the WHI estrogen-alone substudy, a statistically significant increased risk of stroke was reported in women 50 to 79 years of age receiving daily CE (0.625 mg)-alone compared to women in the same age group receiving placebo (45 versus 33 per 10,000 women-years). The increase in risk was demonstrated in Year 1 and persisted [see Clinical Studies (14.5)]. Should a stroke occur or be suspected, estrogen-alone therapy should be discontinued immediately.

Subgroup analyses of women 50 to 59 years of age suggest no increased risk of stroke for those women receiving CE (0.625 mg)-alone versus those receiving placebo (18 versus 21 per 10,000 women-years).^1

In the WHI estrogen plus progestin substudy, a statistically significant increased risk of stroke was reported in women 50 to 79 years of age receiving daily CE (0.625 mg) plus MPA (2.5 mg) compared to women in the same age group receiving placebo (33 versus 25 per 10,000 women-years) [see Clinical Studies (14.5)]. The increase in risk was demonstrated after the first year and persisted.^1 Should a stroke occur or be suspected, estrogen plus progestin therapy should be discontinued immediately.

Coronary Heart Disease

In the WHI estrogen-alone substudy, no overall effect on coronary heart disease (CHD) events (defined as nonfatal MI, silent MI, or CHD death) was reported in women receiving estrogen-alone compared to placebo^2 [see Clinical Studies (14.5)].

Subgroup analyses of women 50 to 59 years of age suggest a statistically non-significant reduction in CHD events (CE [0.625 mg]-alone compared to placebo) in women with less than 10 years since menopause (8 versus 16 per 10,000 women-years).^1

In the WHI estrogen plus progestin substudy, there was a statistically non-significant increased risk of CHD events reported in women receiving daily CE (0.625 mg) plus MPA (2.5 mg) compared to women receiving placebo (41 versus 34 per 10,000 women-years).^1 An increase in relative risk was demonstrated in Year 1, and a trend toward decreasing relative risk was reported in years 2 through 5 [see Clinical Studies (14.5)].

In postmenopausal women with documented heart disease (n = 2,763, average 66.7 years of age), in a controlled clinical trial of secondary prevention of cardiovascular disease (Heart and Estrogen/Progestin Replacement Study; HERS), treatment with daily CE (0.625 mg) plus MPA (2.5 mg) demonstrated no cardiovascular benefit. During an average follow-up of 4.1 years, treatment with CE plus MPA did not reduce the overall rate of CHD events in postmenopausal women with established CHD. There were more CHD events in the CE plus MPA‑treated group than in the placebo group in Year 1, but not during the subsequent years. Two thousand, three hundred and twenty-one (2,321) women from the original HERS trial agreed to participate in an open label extension of HERS, HERS II. Average follow-up in HERS II was an additional 2.7 years, for a total of 6.8 years overall. Rates of CHD events were comparable among women in the CE (0.625 mg) plus MPA (2.5 mg) group and the placebo group in HERS, HERS II, and overall.

Venous Thromboembolism (VTE)

In the WHI estrogen-alone substudy, the risk of VTE (DVT and PE), was increased for women receiving daily CE (0.625 mg)-alone compared to placebo (30 versus 22 per 10,000 women-years), although only the increased risk of DVT reached statistical significance (23 versus 15 per 10,000 women-years). The increase in VTE risk was demonstrated during the first 2 years^3 [see Clinical Studies (14.5)]. Should a VTE occur or be suspected, estrogen-alone therapy should be discontinued immediately.

In the WHI estrogen plus progestin substudy, a statistically significant 2-fold greater rate of VTE was reported in women receiving daily CE (0.625 mg) plus MPA (2.5 mg) compared to women receiving placebo (35 versus 17 per 10,000 women-years). Statistically significant increases in risk for both DVT (26 versus 13 per 10,000 women-years) and PE (18 versus 8 per 10,000 women-years) were also demonstrated. The increase in VTE risk was demonstrated during the first year and persisted^4 [see Clinical Studies (14.5)]. Should a VTE occur or be suspected, estrogen plus progestin therapy should be discontinued immediately.

If feasible, estrogens should be discontinued at least 4 to 6 weeks before surgery of the type associated with an increased risk of thromboembolism, or during periods of prolonged immobilization.

5.2 Malignant Neoplasms

Endometrial Cancer

An increased risk of endometrial cancer has been reported with the use of unopposed estrogen therapy in a woman with a uterus. The reported endometrial cancer risk among unopposed estrogen users is about 2 to 12 times greater than in non-users, and appears dependent on duration of treatment and on estrogen dose. Most studies show no significant increased risk associated with use of estrogens for less than 1 year. The greatest risk appears to be associated with prolonged use, with increased risks of 15- to 24-fold for 5 to 10 years or more, and this risk has been shown to persist for at least 8 to 15 years after estrogen therapy is discontinued.

Clinical surveillance of all women using estrogen-alone or estrogen plus progestin therapy is important. Adequate diagnostic measures, including directed or random endometrial sampling when indicated, should be undertaken to rule out malignancy in postmenopausal women with undiagnosed persistent or recurring abnormal genital bleeding. There is no evidence that the use of natural estrogens results in a different endometrial risk profile than synthetic estrogens of equivalent estrogen dose. Adding a progestin to postmenopausal estrogen therapy has been shown to reduce the risk of endometrial hyperplasia, which may be a precursor to endometrial cancer.

Breast Cancer

The WHI substudy of daily CE (0.625 mg)-alone provided information about breast cancer in estrogen-alone users. In the WHI estrogen-alone substudy, after an average follow-up of 7.1 years, daily CE (0.625 mg)-alone was not associated with an increased risk of invasive breast cancer [relative risk (RR) 0.80]^5 [see Clinical Studies (14.5)].

After a mean follow-up of 5.6 years, the estrogen plus progestin substudy reported an increased risk of invasive breast cancer in women who took daily CE plus MPA. In this substudy, prior use of estrogen-alone or estrogen plus progestin therapy was reported by 26% of the women. The relative risk of invasive breast cancer was 1.24, and the absolute risk was 41 versus 33 cases per 10,000 women-years, for CE plus MPA compared with placebo.^6

Among women who reported prior use of hormone therapy, the relative risk of invasive breast cancer was 1.86, and the absolute risk was 46 versus 25 cases per 10,000 women-years for CE plus MPA compared with placebo. Among women who reported no prior use of hormone therapy, the relative risk of invasive breast cancer was 1.09, and the absolute risk was 40 versus 36 cases per 10,000 women-years for CE plus MPA compared with placebo. In the same substudy, invasive breast cancers were larger, were more likely to be node positive, and were diagnosed at a more advanced stage in the CE (0.625 mg) plus MPA (2.5 mg) group compared with the placebo group. Metastatic disease was rare, with no apparent difference between the two groups. Other prognostic factors, such as histologic subtype, grade and hormone receptor status did not differ between the groups [see Clinical Studies (14.5)].

Consistent with the WHI clinical trials, observational studies have also reported an increased risk of breast cancer for estrogen plus progestin therapy, and a smaller increased risk for estrogen-alone therapy, after several years of use. One large meta-analysis of prospective cohort studies reported increased risks that were dependent upon duration of use and could last up to >10 years after discontinuation of estrogen plus progestin therapy and estrogen‑alone therapy. Extension of the WHI trials also demonstrated increased breast cancer risk associated with estrogen plus progestin therapy. Observational studies also suggest that the risk of breast cancer was greater, and became apparent earlier, with estrogen plus progestin therapy as compared to estrogen-alone therapy. However, these studies have not found significant variation in the risk of breast cancer among different estrogen plus progestin combinations, doses, or routes of administration.

The use of estrogen-alone and estrogen plus progestin has been reported to result in an increase in abnormal mammograms, requiring further evaluation.

All women should receive yearly breast examinations by a healthcare provider and perform monthly breast self‑examinations. In addition, mammography examinations should be scheduled based on patient age, risk factors, and prior mammogram results.

Ovarian Cancer

The WHI estrogen plus progestin substudy reported a statistically non-significant increased risk of ovarian cancer. After an average follow-up of 5.6 years, the relative risk for ovarian cancer for CE plus MPA versus placebo was 1.58 (95% confidence interval [CI] 0.77–3.24). The absolute risk for CE plus MPA versus placebo was 4 versus 3 cases per 10,000 women-years.^7

A meta-analysis of 17 prospective and 35 retrospective epidemiology studies found that women who used hormonal therapy for menopausal symptoms had an increased risk for ovarian cancer. The primary analysis, using case-control comparisons, included 12,110 cancer cases from the 17 prospective studies. The relative risks associated with current use of hormonal therapy was 1.41 (95% CI 1.32 to 1.50); there was no difference in the risk estimates by duration of the exposure (less than 5 years [median of 3 years] vs. greater than 5 years [median of 10 years] of use before the cancer diagnosis). The relative risk associated with combined current and recent use (discontinued use within 5 years before cancer diagnosis) was 1.37 (95% CI 1.27–1.48), and the elevated risk was significant for both estrogen-alone and estrogen plus progestin products. The exact duration of hormone therapy use associated with an increased risk of ovarian cancer, however, is unknown.

5.3 Probable Dementia

In the WHIMS estrogen-alone ancillary study of WHI, a population of 2,947 hysterectomized women 65 to 79 years of age was randomized to daily CE (0.625 mg)-alone or placebo.

After an average follow-up of 5.2 years, 28 women in the estrogen-alone group and 19 women in the placebo group were diagnosed with probable dementia. The relative risk of probable dementia for CE-alone versus placebo was 1.49 (95% CI 0.83–2.66). The absolute risk of probable dementia for CE-alone versus placebo was 37 versus 25 cases per 10,000 women-years^8 [see Use in Specific Populations (8.5), and Clinical Studies (14.6)].

In the WHIMS estrogen plus progestin ancillary study of WHI, a population of 4,532 postmenopausal women 65 to 79 years of age was randomized to daily CE (0.625 mg) plus MPA (2.5 mg) or placebo. After an average follow-up of 4 years, 40 women in the CE plus MPA group and 21 women in the placebo group were diagnosed with probable dementia. The relative risk of probable dementia for CE plus MPA versus placebo was 2.05 (95% CI 1.21–3.48). The absolute risk of probable dementia for CE plus MPA versus placebo was 45 versus 22 cases per 10,000 women-years^8 [see Use in Specific Populations (8.5), and Clinical Studies (14.6)].

When data from the two populations in the WHIMS estrogen-alone and estrogen plus progestin ancillary studies were pooled as planned in the WHIMS protocol, the reported overall relative risk for probable dementia was 1.76 (95% CI 1.19–2.60). Since both substudies were conducted in women 65 to 79 years of age, it is unknown whether these findings apply to younger postmenopausal women^8 [see Use in Specific Populations (8.5), and Clinical Studies (14.6)].

5.4 Gallbladder Disease

A 2- to 4-fold increase in the risk of gallbladder disease requiring surgery in postmenopausal women receiving estrogens has been reported.

5.5 Hypercalcemia

Estrogen administration may lead to severe hypercalcemia in patients with breast cancer and bone metastases. If hypercalcemia occurs, use of the drug should be stopped and appropriate measures taken to reduce the serum calcium level.

5.6 Visual Abnormalities

Retinal vascular thrombosis has been reported in patients receiving estrogens. Discontinue medication pending examination if there is sudden partial or complete loss of vision, or a sudden onset of proptosis, diplopia, or migraine. If examination reveals papilledema or retinal vascular lesions, estrogens should be permanently discontinued.

5.7 Anaphylactic Reaction and Angioedema

Cases of anaphylaxis, which developed within minutes to hours after taking PREMARIN and require emergency medical management, have been reported in the postmarketing setting. Skin (hives, pruritis, swollen lips-tongue-face) and either respiratory tract (respiratory compromise) or gastrointestinal tract (abdominal pain, vomiting) involvement has been noted.

Angioedema involving the tongue, larynx, face, hands, and feet requiring medical intervention has occurred postmarketing in patients taking PREMARIN. If angioedema involves the tongue, glottis, or larynx, airway obstruction may occur. Patients who develop an anaphylactic reaction with or without angioedema after treatment with PREMARIN should not receive PREMARIN again.

5.8 Addition of a Progestin When a Woman Has Not Had a Hysterectomy

Studies of the addition of a progestin for 10 or more days of a cycle of estrogen administration or daily with estrogen in a continuous regimen, have reported a lowered incidence of endometrial hyperplasia than would be induced by estrogen treatment alone. Endometrial hyperplasia may be a precursor to endometrial cancer.

There are, however, possible risks that may be associated with the use of progestins with estrogens compared to estrogen-alone regimens. These include an increased risk of breast cancer.

5.9 Elevated Blood Pressure

In a small number of case reports, substantial increases in blood pressure have been attributed to idiosyncratic reactions to estrogens. In a large, randomized, placebo-controlled clinical trial, a generalized effect of estrogen therapy on blood pressure was not seen.

5.10 Exacerbation of Hypertriglyceridemia

In women with pre-existing hypertriglyceridemia, estrogen therapy may be associated with elevations of plasma triglycerides leading to pancreatitis. Consider discontinuation of treatment if pancreatitis occurs.

5.11 Hepatic Impairment and/or Past History of Cholestatic Jaundice

Estrogens may be poorly metabolized in patients with impaired liver function. For women with a history of cholestatic jaundice associated with past estrogen use or with pregnancy, caution should be exercised, and in the case of recurrence, medication should be discontinued.

5.12 Exacerbation of Hypothyroidism

Estrogen administration leads to increased thyroid-binding globulin (TBG) levels. Women with normal thyroid function can compensate for the increased TBG by making more thyroid hormone, thus maintaining free T4 and T3 serum concentrations in the normal range. Women dependent on thyroid hormone replacement therapy who are also receiving estrogens may require increased doses of their thyroid replacement therapy. These women should have their thyroid function monitored in order to maintain their free thyroid hormone levels in an acceptable range.

5.13 Fluid Retention

Estrogens may cause some degree of fluid retention. Women with conditions that might be influenced by this factor, such as a cardiac or renal dysfunction, warrant careful observation when estrogens are prescribed.

5.14 Hypocalcemia

Estrogen therapy should be used with caution in all patients with hypoparathyroidism as estrogen-induced hypocalcemia may occur.

5.15 Hereditary Angioedema

Exogenous estrogens may exacerbate symptoms of angioedema in women with hereditary angioedema.

5.16 Exacerbation of Endometriosis

A few cases of malignant transformation of residual endometrial implants have been reported in women treated post-hysterectomy with estrogen-alone therapy. For women known to have residual endometriosis post-hysterectomy, the addition of progestin should be considered.

5.17 Exacerbation of Other Conditions

Estrogen therapy may cause an exacerbation of asthma, diabetes mellitus, epilepsy, migraine, porphyria, systemic lupus erythematosus, and hepatic hemangiomas and should be used with caution in women with these conditions.

5.18 Laboratory Tests

Serum follicle stimulating hormone (FSH) and estradiol levels have not been shown to be useful in the management of moderate to severe vasomotor symptoms and moderate to severe symptoms of vulvar and vaginal atrophy.

Laboratory parameters may be useful in guiding dosage for the treatment of hypoestrogenism due to hypogonadism, castration and primary ovarian failure.

5.19 Drug-Laboratory Test Interactions

- Accelerated prothrombin time, partial thromboplastin time, and platelet aggregation time; increased platelet count; increased factors II, VII antigen, VIII antigen, VIII coagulant activity, IX, X, XII, VII‑X complex, II-VII-X complex, and beta-thromboglobulin; decreased levels of anti-factor Xa and antithrombin III, decreased antithrombin III activity; increased levels of fibrinogen and fibrinogen activity; increased plasminogen antigen and activity.
- Increased thyroid-binding globulin (TBG) levels leading to increased circulating total thyroid hormone levels as measured by protein-bound iodine (PBI), T4 levels (by column or by radioimmunoassay) or T3 levels by radioimmunoassay. T3 resin uptake is decreased, reflecting the elevated TBG. Free T4 and free T3 concentrations are unaltered. Patients on thyroid replacement therapy may require higher doses of thyroid hormone.
- Other binding proteins may be elevated in serum, for example, corticosteroid binding globulin (CBG), sex hormone-binding globulin (SHBG), leading to increased total circulating corticosteroids and sex steroids, respectively. Free hormone concentrations, such as testosterone and estradiol, may be decreased. Other plasma proteins may be increased (angiotensinogen/renin substrate, alpha‑1‑antitrypsin, ceruloplasmin).
- Increased plasma high-density lipoprotein (HDL) and HDL2 cholesterol subfraction, reduced low‑density lipoprotein (LDL) cholesterol, increased triglyceride levels.
- Impaired glucose tolerance.

6 ADVERSE REACTIONS

The following serious adverse reactions are discussed elsewhere in labeling:

- Cardiovascular Disorders [see Boxed Warning, Warnings and Precautions (5.1)]
- Malignant Neoplasms [see Boxed Warning, Warnings and Precautions (5.2)]

6.1 Clinical Study Experience

Because clinical trials are conducted under widely varying conditions, adverse reaction rates observed in the clinical trials of a drug cannot be directly compared to rates in the clinical trials of another drug and may not reflect the rates observed in clinical practice.

During the first year of a 2-year clinical trial with 2,333 postmenopausal women with a uterus between 40 and 65 years of age (88% Caucasian), 1,012 women were treated with CE, and 332 were treated with placebo.

Table 1 summarizes treatment-related adverse reactions that occurred at a rate of ≥1% in any treatment group.

Table 1: Treatment-Related Adverse Reactions at a Frequency ≥1%
 | PREMARIN 0.625 mg (n=348) | PREMARIN 0.45 mg (n=338) | PREMARIN 0.3 mg (n=326) | Placebo (n=332)
Body as a whole
Abdominal pain | 38 (11) | 28 (8) | 30 (9) | 21 (6)
Asthenia | 16 (5) | 8 (2) | 14 (4) | 3 (1)
Back pain | 18 (5) | 11 (3) | 13 (4) | 4 (1)
Chest pain | 2 (1) | 3 (1) | 4 (1) | 2 (1)
Generalized edema | 7 (2) | 6 (2) | 4 (1) | 8 (2)
Headache | 45 (13) | 47 (14) | 44 (13) | 46 (14)
Moniliasis | 5 (1) | 4 (1) | 4 (1) | 1 (0)
Pain | 17 (5) | 10 (3) | 12 (4) | 14 (4)
Pelvic pain | 10 (3) | 9 (3) | 8 (2) | 4 (1)
Cardiovascular system
Hypertension | 4 (1) | 4 (1) | 7 (2) | 5 (2)
Migraine | 7 (2) | 1 (0) | 0 | 3 (1)
Palpitation | 3 (1) | 3 (1) | 3 (1) | 4 (1)
Vasodilatation | 2 (1) | 2 (1) | 3 (1) | 5 (2)
Digestive system
Constipation | 7 (2) | 6 (2) | 4 (1) | 3 (1)
Diarrhea | 4 (1) | 5 (1) | 5 (2) | 8 (2)
Dyspepsia | 7 (2) | 5 (1) | 6 (2) | 14 (4)
Eructation | 1 (0) | 1 (0) | 4 (1) | 1 (0)
Flatulence | 22 (6) | 18 (5) | 13 (4) | 8 (2)
Increased appetite | 4 (1) | 1 (0) | 1 (0) | 2 (1)
Nausea | 16 (5) | 10 (3) | 15 (5) | 16 (5)
Metabolic and nutritional
Hyperlipidemia | 2 (1) | 4 (1) | 3 (1) | 2 (1)
Peripheral edema | 5 (1) | 2 (1) | 4 (1) | 3 (1)
Weight gain | 11 (3) | 10 (3) | 8 (2) | 14 (4)
Musculoskeletal system
Arthralgia | 6 (2) | 3 (1) | 2 (1) | 5 (2)
Leg cramps | 10 (3) | 5 (1) | 9 (3) | 4 (1)
Myalgia | 2 (1) | 1 (0) | 4 (1) | 1 (0)
Nervous system
Anxiety | 6 (2) | 4 (1) | 2 (1) | 4 (1)
Depression | 17 (5) | 15 (4) | 10 (3) | 17 (5)
Dizziness | 9 (3) | 7 (2) | 4 (1) | 5 (2)
Emotional lability | 3 (1) | 4 (1) | 5 (2) | 8 (2)
Hypertonia | 1 (0) | 1 (0) | 5 (2) | 3 (1)
Insomnia | 16 (5) | 10 (3) | 13 (4) | 14 (4)
Nervousness | 9 (3) | 12 (4) | 2 (1) | 6 (2)
Skin and appendages
Acne | 3 (1) | 1 (0) | 8 (2) | 3 (1)
Alopecia | 6 (2) | 6 (2) | 5 (2) | 2 (1)
Hirsutism | 4 (1) | 2 (1) | 1 (0) | 0
Pruritus | 11 (3) | 11 (3) | 10 (3) | 3 (1)
Rash | 6 (2) | 3 (1) | 1 (0) | 2 (1)
Skin discoloration | 4 (1) | 2 (1) | 0 | 1 (0)
Sweating | 4 (1) | 1 (0) | 3 (1) | 4 (1)
Urogenital system
Breast disorder | 6 (2) | 3 (1) | 3 (1) | 6 (2)
Breast enlargement | 3 (1) | 4 (1) | 7 (2) | 3 (1)
Breast neoplasm | 4 (1) | 4 (1) | 7 (2) | 7 (2)
Breast pain | 37 (11) | 39 (12) | 24 (7) | 26 (8)
Cervix disorder | 8 (2) | 4 (1) | 5 (2) | 0
Dysmenorrhea | 12 (3) | 10 (3) | 4 (1) | 2 (1)
Endometrial disorder | 4 (1) | 2 (1) | 2 (1) | 0
Endometrial hyperplasia | 16 (5) | 8 (2) | 1 (0) | 0
Leukorrhea | 17 (5) | 17 (5) | 12 (4) | 6 (2)
Metrorrhagia | 11 (3) | 4 (1) | 3 (1) | 1 (0)
Urinary tract infection | 1 (0) | 2 (1) | 1 (0) | 4 (1)
Uterine fibroids enlarged | 6 (2) | 1 (0) | 2 (1) | 2 (1)
Uterine spasm | 11 (3) | 5 (1) | 3 (1) | 2 (1)
Vaginal dryness | 1 (0) | 2 (1) | 1 (0) | 6 (2)
Vaginal hemorrhage | 46 (13) | 13 (4) | 6 (2) | 0
Vaginal moniliasis | 14 (4) | 10 (3) | 12 (4) | 5 (2)
Vaginitis | 18 (5) | 7 (2) | 9 (3) | 1 (0)

6.2 Postmarketing Experience

The following additional adverse reactions have been identified during post-approval use of PREMARIN. Because these reactions are reported voluntarily from a population of uncertain size, it is not possible always to reliably estimate their frequency or establish a causal relationship to drug exposure.

Genitourinary system

Abnormal uterine bleeding; dysmenorrheal or pelvic pain, increase in size of uterine leiomyomata, vaginitis, including vaginal candidiasis, change in cervical secretion, ovarian cancer, endometrial hyperplasia, endometrial cancer, leukorrhea.

Breasts

Tenderness, enlargement, pain, discharge, galactorrhea, fibrocystic breast changes, breast cancer, gynecomastia in males.

Cardiovascular

Deep and superficial venous thrombosis, pulmonary embolism, thrombophlebitis, myocardial infarction, stroke, increase in blood pressure.

Gastrointestinal

Nausea, vomiting, abdominal pain, bloating, cholestatic jaundice, increased incidence of gallbladder disease, pancreatitis, enlargement of hepatic hemangiomas, ischemic colitis.

Skin

Chloasma or melasma that may persist when drug is discontinued, erythema multiforme, erythema nodosum, loss of scalp hair, hirsutism, pruritus, rash.

Eyes

Retinal vascular thrombosis, intolerance to contact lenses.

Central nervous system

Headache, migraine, dizziness , mental depression, nervousness, mood disturbances, irritability, exacerbation of epilepsy, dementia, possible growth potentiation of benign meningioma.

Miscellaneous

Increase or decrease in weight, glucose intolerance, aggravation of porphyria, edema, arthralgias, leg cramps, changes in libido, urticaria, exacerbation of asthma, increased triglycerides, hypersensitivity.

7 DRUG INTERACTIONS

Data from a single-dose drug-drug interaction study involving CE and MPA indicate that the pharmacokinetic disposition of both drugs is not altered when the drugs are coadministered. No other clinical drug-drug interaction studies have been conducted with CE.

7.1 Metabolic Interactions

In vitro and in vivo studies have shown that estrogens are metabolized partially by cytochrome P450 3A4 (CYP3A4). Therefore, inducers or inhibitors of CYP3A4 may affect estrogen drug metabolism. Inducers of CYP3A4, such as St. John's Wort (Hypericum perforatum) preparations, phenobarbital, carbamazepine, and rifampin, may reduce plasma concentrations of estrogens, possibly resulting in a decrease in therapeutic effects and/or changes in the uterine bleeding profile. Inhibitors of CYP3A4, such as erythromycin, clarithromycin, ketoconazole, itraconazole, ritonavir and grapefruit juice, may increase plasma concentrations of estrogens and may result in side effects.

8 USE IN SPECIFIC POPULATIONS

8.1 Pregnancy

Risk Summary

PREMARIN is not indicated for use during pregnancy.

There are no data with the use of PREMARIN tablet in pregnant women; however, epidemiologic studies and meta-analyses have not found an increased risk of genital or nongenital birth defects (including cardiac anomalies and limb-reduction defects) following exposure to combined hormonal contraceptives (estrogen and progestins) before conception or during early pregnancy.

In the U.S. general population, the estimated background risk of major birth defects and miscarriage in clinically recognized pregnancies is 2% to 4% and 15% to 20%, respectively.

8.2 Lactation

Risk Summary

Estrogens and progestins and metabolites are present in human milk. These hormones can reduce milk production in breast-feeding women. This reduction can occur at any time but is less likely to occur once breast-feeding is well established. The developmental and health benefits of breast‑feeding should be considered along with the mother’s clinical need for PREMARIN and any potential adverse effects on the breast-fed child from PREMARIN or from the underlying maternal condition.

8.4 Pediatric Use

Estrogen therapy has been used for the induction of puberty in adolescents with some forms of pubertal delay. Safety and effectiveness in pediatric patients have not otherwise been established.

Large and repeated doses of estrogen over an extended time period have been shown to accelerate epiphyseal closure, which could result in short stature if treatment is initiated before the completion of physiologic puberty in normally developing children. If estrogen is administered to patients whose bone growth is not complete, periodic monitoring of bone maturation and effects on epiphyseal centers is recommended during estrogen administration.

Estrogen treatment of prepubertal girls also induces premature breast development and vaginal cornification, and may induce vaginal bleeding. In boys, estrogen treatment may modify the normal pubertal process and induce gynecomastia.

8.5 Geriatric Use

There have not been sufficient numbers of geriatric patients involved in studies utilizing PREMARIN to determine whether those over 65 years of age differ from younger subjects in their response to PREMARIN.

The Women's Health Initiative Study

In the WHI estrogen-alone substudy (daily CE 0.625 mg-alone versus placebo), there was a higher relative risk of stroke in women greater than 65 years of age [see Clinical Studies (14.5)].

In the WHI estrogen plus progestin substudy (daily CE [0.625 mg] plus MPA [2.5 mg] versus placebo), there was a higher relative risk of nonfatal stroke and invasive breast cancer in women greater than 65 years of age [see Clinical Studies (14.5)].

The Women's Health Initiative Memory Study

In the WHIMS ancillary studies of postmenopausal women 65 to 79 years of age, there was an increased risk of developing probable dementia in women receiving estrogen-alone or estrogen plus progestin when compared to placebo [see Warnings and Precautions (5.3), and Clinical Studies (14.6)].

Since both ancillary studies were conducted in women 65 to 79 years of age, it is unknown whether these findings apply to younger postmenopausal women^8 [see Warnings and Precautions (5.3), and Clinical Studies (14.6)].

8.6 Renal Impairment

The effect of renal impairment on the pharmacokinetics of PREMARIN has not been studied.

8.7 Hepatic Impairment

The effect of hepatic impairment on the pharmacokinetics of PREMARIN has not been studied.

10 OVERDOSAGE

Overdosage of estrogen may cause nausea, vomiting, breast tenderness, abdominal pain, drowsiness and fatigue, and withdrawal bleeding may occur in women. Treatment of overdose consists of discontinuation of PREMARIN therapy with institution of appropriate symptomatic care.

11 DESCRIPTION

PREMARIN® (conjugated estrogens tablets, USP) for oral administration contains a mixture of CE purified from pregnant mares' urine and consists of the sodium salts of water-soluble estrogen sulfates blended to represent the average composition of material derived from pregnant mares' urine. It is a mixture of sodium estrone sulfate and sodium equilin sulfate. It contains concomitant components as sodium sulfate conjugates, 17α-dihydroequilin, 17α estradiol, and 17β-dihydroequilin. Tablets for oral administration are available in 0.3 mg, 0.45 mg, 0.625 mg, 0.9 mg, and 1.25 mg strengths of CE.

PREMARIN 0.3 mg, 0.45 mg, 0.625 mg, 0.9 mg, and 1.25 mg tablets also contain the following inactive ingredients: calcium phosphate tribasic, carnauba wax, hydroxypropyl cellulose, hypromellose, lactose monohydrate, magnesium stearate, microcrystalline cellulose, polyethylene glycol, powdered cellulose, sucrose, and titanium dioxide. Each tablet strength contains the following colors:

Tablet strength | Tablet color contains
0.3 mg | D&C Yellow No. 10 and FD&C Blue No. 2
0.45 mg | FD&C Blue No. 2
0.625 mg | FD&C Blue No. 2 and FD&C Red No. 40
0.9 mg | D&C Red No. 30 and D&C Red No. 7
1.25 mg | Black iron oxide, D&C Yellow No. 10 and FD&C Yellow No. 6

PREMARIN tablets comply with USP Dissolution Test criteria, as outlined below:

PREMARIN 1.25 mg tablets | USP Dissolution Test 4
PREMARIN 0.3 mg, 0.45 mg and 0.625 mg tablets | USP Dissolution Test 5
PREMARIN 0.9 mg tablets | USP Dissolution Test 6

12 CLINICAL PHARMACOLOGY

12.1 Mechanism of Action

Endogenous estrogens are largely responsible for the development and maintenance of the female reproductive system and secondary sexual characteristics. Although circulating estrogens exist in a dynamic equilibrium of metabolic interconversions, estradiol is the principal intracellular human estrogen and is substantially more potent than its metabolites, estrone and estriol, at the receptor level.

The primary source of estrogen in normally cycling adult women is the ovarian follicle, which secretes 70 to 500 mcg of estradiol daily, depending on the phase of the menstrual cycle. After menopause, most endogenous estrogen is produced by conversion of androstenedione, secreted by the adrenal cortex, to estrone in the peripheral tissues. Thus, estrone and the sulfate-conjugated form, estrone sulfate, are the most abundant circulating estrogens in postmenopausal women.

Estrogens act through binding to nuclear receptors in estrogen-responsive tissues. To date, two estrogen receptors have been identified. These vary in proportion from tissue to tissue.

Circulating estrogens modulate the pituitary secretion of the gonadotropins, luteinizing hormone (LH) and FSH, through a negative feedback mechanism. Estrogens act to reduce the elevated levels of these gonadotropins seen in postmenopausal women.

12.2 Pharmacodynamics

There are no pharmacodynamic data for PREMARIN.

12.3 Pharmacokinetics

Absorption

Conjugated estrogens are water-soluble and are absorbed from the gastrointestinal tract after release from the drug formulation. The PREMARIN tablet releases CE slowly over several hours. Table 2 summarizes the mean pharmacokinetic parameters for unconjugated and CE following administration of 1 × 0.625 mg and 1 × 1.25 mg tablets to healthy postmenopausal women.

Food effect: The pharmacokinetics of PREMARIN 0.45 mg and 1.25 mg tablets were assessed following a single dose with a high-fat breakfast and with fasting administration. The Cmax and AUC of estrogens were altered approximately 3–13%. The changes to Cmax and AUC are not considered clinically meaningful, therefore PREMARIN may be taken without regard to meals.

Table 2: Pharmacokinetic Parameters for PREMARIN
Pharmacokinetic Profile of Unconjugated Estrogens Following a Dose of 1 × 0.625 mg
PK Parameter Arithmetic Mean (%CV) | Cmax (pg/mL) | tmax (h) | t1/2 (h) | AUC (pg∙h/mL)
Estrone | 87 (33) | 9.6 (33) | 50.7 (35) | 5557 (59)
Baseline-adjusted estrone | 64 (42) | 9.6 (33) | 20.2 (40) | 1723 (52)
Equilin | 31 (38) | 7.9 (32) | 12.9 (112) | 602 (54)
Pharmacokinetic Profile of CE Following a Dose of 1 × 0.625 mg
PK Parameter Arithmetic Mean (%CV) | Cmax (ng/mL) | tmax (h) | t1/2 (h) | AUC (ng∙h/mL)
Total Estrone | 2.7 (43) | 6.9 (25) | 26.7 (33) | 75 (52)
Baseline-adjusted total estrone | 2.5 (45) | 6.9 (25) | 14.8 (35) | 46 (48)
Total Equilin | 1.8 (56) | 5.6 (45) | 11.4 (31) | 27 (56)
Pharmacokinetic Profile of Unconjugated Estrogens Following a Dose of 1 × 1.25 mg
PK Parameter Arithmetic Mean (%CV) | Cmax (pg/mL) | tmax (h) | t1/2 (h) | AUC (pg∙h/mL)
Estrone | 124 (30) | 10.0 (32) | 38.1 (37) | 6332 (44)
Baseline-adjusted estrone | 102 (35) | 10.0 (32) | 19.7 (48) | 3159 (53)
Equilin | 59 (43) | 8.8 (36) | 10.9 (47) | 1182 (42)
Pharmacokinetic Profile of CE Following a Dose of 1 × 1.25 mg
PK Parameter Arithmetic Mean (%CV) | Cmax (ng/mL) | tmax (h) | t1/2 (h) | AUC (ng∙h/mL)
Total Estrone | 4.5 (39) | 8.2 (58) | 26.5 (40) | 109 (46)
Baseline-adjusted total estrone | 4.3 (41) | 8.2 (58) | 17.5 (41) | 87 (44)
Total equilin | 2.9 (42) | 6.8 (49) | 12.5 (34) | 48 (51)

Distribution

The distribution of exogenous estrogens is similar to that of endogenous estrogens. Estrogens are widely distributed in the body and are generally found in higher concentration in the sex hormone target organs. Estrogens circulate in the blood largely bound to SHBG and albumin.

Metabolism

Exogenous estrogens are metabolized in the same manner as endogenous estrogens. Circulating estrogens exist in a dynamic equilibrium of metabolic interconversions. These transformations take place mainly in the liver. Estradiol is converted reversibly to estrone, and both can be converted to estriol, which is a major urinary metabolite. Estrogens also undergo enterohepatic recirculation via sulfate and glucuronide conjugation in the liver, biliary secretion of conjugates into the intestine, and hydrolysis in the intestine followed by reabsorption. In postmenopausal women, a significant proportion of the circulating estrogens exist as sulfate conjugates, especially estrone sulfate, which serves as a circulating reservoir for the formation of more active estrogens.

Excretion

Estradiol, estrone, and estriol are excreted in the urine, along with glucuronide and sulfate conjugates.

Use in Specific Populations

No pharmacokinetic studies were conducted with PREMARIN in specific populations, including patients with renal or hepatic impairment.

13 NONCLINICAL TOXICOLOGY

13.1 Carcinogenesis, Mutagenesis, Impairment of Fertility

Long-term continuous administration of natural and synthetic estrogens in certain animal species increases the frequency of carcinomas of the breast, uterus, cervix, vagina, testis, and liver [see Warnings and Precautions (5.2)].

14 CLINICAL STUDIES

14.1 Effects on Vasomotor Symptoms

In the first year of the Health and Osteoporosis, Progestin and Estrogen (HOPE) Study, a total of 2,805 postmenopausal women (average age 53.3 ± 4.9 years) were randomly assigned to one of eight treatment groups of either placebo or CE, with or without MPA. Efficacy for vasomotor symptoms was assessed during the first 12 weeks of treatment in a subset of symptomatic women (n = 241) who had at least seven moderate to severe hot flushes daily, or at least 50 moderate to severe hot flushes during the week before randomization. PREMARIN (0.3 mg, 0.45 mg, and 0.625 mg tablets) was shown to be statistically better than placebo at weeks 4 and 12 for relief of both frequency and severity of moderate to severe vasomotor symptoms. Table 3 shows the adjusted mean number of hot flushes in the PREMARIN 0.3 mg, 0.45 mg, and 0.625 mg and placebo groups during the initial 12-week period.

Table 3: Summary Tabulation of the Number of Hot Flushes Per Day – Mean Values and Comparisons Between the Active Treatment Groups and the Placebo Group: Patients with at Least 7 Moderate to Severe Flushes Per Day or at Least 50 Per Week at Baseline, Last Observation Carried Forward (LOCF)
Treatment (No. of Patients) | ---------------No. of Hot Flushes/Day---------------
Time Period (week) | Baseline Mean ± SD | Observed Mean ± SD | Mean Change ± SD | p-Values vs Placebo [Based on analysis of covariance with treatment as factor and baseline as covariate.]
0.625 mg CE (n = 27)
4 | 12.29 ± 3.89 | 1.95 ± 2.77 | -10.34 ± 4.73 | <0.001
12 | 12.29 ± 3.89 | 0.75 ± 1.82 | -11.54 ± 4.62 | <0.001
0.45 mg CE (n = 32)
4 | 12.25 ± 5.04 | 5.04 ± 5.31 | -7.21 ± 4.75 | <0.001
12 | 12.25 ± 5.04 | 2.32 ± 3.32 | -9.93 ± 4.64 | <0.001
0.3 mg CE (n = 30)
4 | 13.77 ± 4.78 | 4.65 ± 3.71 | -9.12 ± 4.71 | <0.001
12 | 13.77 ± 4.78 | 2.52 ± 3.23 | -11.25 ± 4.60 | <0.001
Placebo (n = 28)
4 | 11.69 ± 3.87 | 7.89 ± 5.28 | -3.80 ± 4.71 | -
12 | 11.69 ± 3.87 | 5.71 ± 5.22 | -5.98 ± 4.60 | -

14.2 Effects on Vulvar and Vaginal Atrophy

Results of vaginal maturation indexes at cycles 6 and 13 showed that the differences from placebo were statistically significant (p < 0.001) for all treatment groups. (CE alone and CE/MPA treatment groups).

14.3 Effects on Bone Mineral Density

Health and Osteoporosis, Progestin and Estrogen (HOPE) Study

The HOPE study was a double-blind, randomized, placebo/active-drug-controlled, multicenter study of healthy postmenopausal women with an intact uterus. Subjects (mean age 53.3 ± 4.9 years) were 2.3 ± 0.9 years on average since menopause and took one 600 mg tablet of elemental calcium (Caltrate™) daily. Subjects were not given Vitamin D supplements. They were treated with PREMARIN 0.625 mg, 0.45 mg, 0.3 mg, or placebo. Prevention of bone loss was assessed by measurement of bone mineral density (BMD), primarily at the anteroposterior lumbar spine (L2 to L4). Secondarily, BMD measurements of the total body, femoral neck, and trochanter were also analyzed. Serum osteocalcin, urinary calcium, and N-telopeptide were used as bone turnover markers (BTM) at cycles 6, 13, 19, and 26.

Intent-to-treat subjects

All active treatment groups showed significant differences from placebo in each of the four BMD endpoints at cycles 6, 13, 19, and 26. The mean percent increases in the primary efficacy measure (L2 to L4 BMD) at the final on-therapy evaluation (cycle 26 for those who completed and the last available evaluation for those who discontinued early) were 2.46% with 0.625 mg, 2.26% with 0.45 mg, and 1.13% with 0.3 mg. The placebo group showed a mean percent decrease from baseline at the final evaluation of 2.45%. These results show that the lower dosages of PREMARIN were effective in increasing L2 to L4 BMD compared with placebo, and therefore support the efficacy of the lower doses.

The analysis for the other three BMD endpoints yielded mean percent changes from baseline in femoral trochanter that were generally larger than those seen for L2 to L4, and changes in femoral neck and total body that were generally smaller than those seen for L2 to L4. Significant differences between groups indicated that each of the PREMARIN treatments was more effective than placebo for all three of these additional BMD endpoints. With regard to femoral neck and total body, the active treatment groups all showed mean percent increases in BMD, while placebo treatment was accompanied by mean percent decreases. For femoral trochanter, each of the PREMARIN dose groups showed a mean percent increase that was significantly greater than the small increase seen in the placebo group. The percent changes from baseline to final evaluation are shown in Table 4.

Table 4: Percent Change in Bone Mineral Density: Comparison Between Active and Placebo Groups in the Intent-to-Treat Population, LOCF
Region Evaluated Treatment Group [Identified by dosage (mg) of PREMARIN or placebo.] | No. of Subjects | Baseline (g/cm^2) Mean ± SD | Change from Baseline (%) Adjusted Mean ± SE | p-Value vs. Placebo
L2 to L4 BMD
0.625 | 83 | 1.17 ± 0.15 | 2.46 ± 0.37 | <0.001
0.45 | 91 | 1.13 ± 0.15 | 2.26 ± 0.35 | <0.001
0.3 | 87 | 1.14 ± 0.15 | 1.13 ± 0.36 | <0.001
Placebo | 85 | 1.14 ± 0.14 | -2.45 ± 0.36
Total Body BMD
0.625 | 84 | 1.15 ± 0.08 | 0.68 ± 0.17 | <0.001
0.45 | 91 | 1.14 ± 0.08 | 0.74 ± 0.16 | <0.001
0.3 | 87 | 1.14 ± 0.07 | 0.40 ± 0.17 | <0.001
Placebo | 85 | 1.13 ± 0.08 | -1.50 ± 0.17
Femoral Neck BMD
0.625 | 84 | 0.91 ± 0.14 | 1.82 ± 0.45 | <0.001
0.45 | 91 | 0.89 ± 0.13 | 1.84 ± 0.44 | <0.001
0.3 | 87 | 0.86 ± 0.11 | 0.62 ± 0.45 | <0.001
Placebo | 85 | 0.88 ± 0.14 | -1.72 ± 0.45
Femoral Trochanter BMD
0.625 | 84 | 0.78 ± 0.13 | 3.82 ± 0.58 | <0.001
0.45 | 91 | 0.76 ± 0.12 | 3.16 ± 0.56 | 0.003
0.3 | 87 | 0.75 ± 0.10 | 3.05 ± 0.57 | 0.005
Placebo | 85 | 0.75 ± 0.12 | 0.81 ± 0.58

Figure 1 shows the cumulative percentage of subjects with changes from baseline equal to or greater than the value shown on the x-axis.

Figure 1. Cumulative Percent of Subjects With Changes From Baseline in Spine BMD of Given Magnitude or Greater in PREMARIN® and Placebo Groups

The mean percent changes from baseline in L2 to L4 BMD for women who completed the bone density study are shown with standard error bars by treatment group in Figure 2. Significant differences between each of the PREMARIN dosage groups and placebo were found at cycles 6, 13, 19, and 26.

Figure 2. Adjusted Mean (SE) Percent Change From Baseline at Each Cycle in Spine BMD: Subjects Completing in PREMARIN Groups and Placebo

The bone turnover markers, serum osteocalcin and urinary N-telopeptide, significantly decreased (p < 0.001) in all active-treatment groups at cycles 6, 13, 19, and 26 compared with the placebo group. Larger mean decreases from baseline were seen with the active groups than with the placebo group. Significant differences from placebo were seen less frequently in urine calcium.

14.4 Effects on Female Hypogonadism

In clinical studies of delayed puberty due to female hypogonadism, breast development was induced by doses as low as 0.15 mg. The dosage may be gradually titrated upward at 6-to 12 month intervals as needed to achieve appropriate bone age advancement and eventual epiphyseal closure. Clinical studies suggest that doses of 0.15 mg, 0.3 mg, and 0.6 mg are associated with mean ratios of bone age advancement to chronological age progression (ΔBA/ΔCA) of 1.1, 1.5, and 2.1, respectively. (PREMARIN in the dose strength of 0.15 mg is not available commercially). Available data suggest that chronic dosing with 0.625 mg is sufficient to induce artificial cyclic menses with sequential progestin treatment and to maintain bone mineral density after skeletal maturity is achieved.

14.5 Women's Health Initiative Studies

The WHI enrolled approximately 27,000 predominantly healthy postmenopausal women in two substudies to assess the risks and benefits of daily oral CE (0.625 mg)-alone or in combination with MPA (2.5 mg) compared to placebo in the prevention of certain chronic diseases. The primary endpoint was the incidence of CHD (defined as nonfatal MI, silent MI and CHD death), with invasive breast cancer as the primary adverse outcome. A "global index" included the earliest occurrence of CHD, invasive breast cancer, stroke, PE, endometrial cancer (only in the CE plus MPA substudy), colorectal cancer, hip fracture, or death due to other causes. These substudies did not evaluate the effects of CE-alone or CE plus MPA on menopausal symptoms.

WHI Estrogen-Alone Substudy

The WHI estrogen-alone substudy was stopped early because an increased risk of stroke was observed, and it was deemed that no further information would be obtained regarding the risks and benefits of estrogen alone in predetermined primary endpoints.

Results of the estrogen-alone substudy, which included 10,739 women (average 63 years of age, range 50 to 79; 75.3% White, 15.1% Black, 6.1% Hispanic, 3.6% Other) after an average follow-up of 7.1 years, are presented in Table 5.

Table 5: Relative and Absolute Risk Seen in the Estrogen Alone Substudy of WHI [Adapted from numerous WHI publications. WHI publications can be viewed at www.nhlbi.nih.gov/whi.]
Event | Relative Risk CE vs. Placebo | CE n = 5,310 | Placebo n = 5,429
 | (95% nCI [Nominal confidence intervals unadjusted for multiple looks and multiple comparisons.]) | Absolute Risk per 10,000 Women-Years
CHD events [Results are based on centrally adjudicated data for an average follow-up of 7.1 years.] | 0.95 (0.78–1.16) | 54 | 57
Non-fatal MI | 0.91 (0.73–1.14) | 40 | 43
CHD death | 1.01 (0.71–1.43) | 16 | 16
All Stroke | 1.33 (1.05–1.68) | 45 | 33
Ischemic stroke | 1.55 (1.19–2.01) | 38 | 25
Deep vein thrombosis, [Not included in "global index."] | 1.47 (1.06–2.06) | 23 | 15
Pulmonary embolism | 1.37 (0.90–2.07) | 14 | 10
Invasive breast cancer | 0.80 (0.62–1.04) | 28 | 34
Colorectal cancer [Results are based on an average follow-up of 6.8 years.] | 1.08 (0.75–1.55) | 17 | 16
Hip fracture | 0.65 (0.45–0.94) | 12 | 19
Vertebral fractures, | 0.64 (0.44–0.93) | 11 | 18
Lower arm/wrist fractures, | 0.58 (0.47–0.72) | 35 | 59
Total fractures, | 0.71 (0.64–0.80) | 144 | 197
Death due to other causes, [All deaths, except from breast or colorectal cancer, definite/probable CHD, PE or cerebrovascular disease.] | 1.08 (0.88–1.32) | 53 | 50
Overall mortality, | 1.04 (0.88–1.22) | 79 | 75
Global Index [A subset of the events was combined in a "global index" defined as the earliest occurrence of CHD events, invasive breast cancer, stroke, pulmonary embolism, colorectal cancer, hip fracture, or death due to other causes.] | 1.02 (0.92–1.13) | 206 | 201

For those outcomes included in the WHI "global index" that reached statistical significance, the absolute excess risk per 10,000 women-years in the group treated with CE-alone was 12 more strokes while the absolute risk reduction per 10,000 women-years was 7 fewer hip fractures.^9 The absolute excess risk of events included in the "global index" was a non-significant 5 events per 10,000 women-years. There was no difference between the groups in terms of all-cause mortality.

No overall difference for primary CHD events (nonfatal MI, silent MI and CHD death) and invasive breast cancer incidence in women receiving CE-alone compared with placebo was reported in final centrally adjudicated results from the estrogen-alone substudy, after an average follow up of 7.1 years. See Table 5.

Centrally adjudicated results for stroke events from the estrogen-alone substudy, after an average follow-up of 7.1 years, reported no significant difference in distribution of stroke subtype or severity, including fatal strokes, in women receiving CE-alone compared to placebo. Estrogen-alone increased the risk for ischemic stroke, and this excess risk was present in all subgroups of women examined.^10

Timing of the initiation of estrogen-alone therapy relative to the start of menopause may affect the overall risk benefit profile. The WHI estrogen-alone substudy stratified by age showed in women 50–59 years of age, a non-significant trend toward reduced risk for CHD [hazard ratio (HR) 0.63 (95% CI 0.36–1.09)] and overall mortality [HR 0.71 (95% CI 0.46–1.11)].

WHI Estrogen Plus Progestin Substudy

The WHI estrogen plus progestin substudy was stopped early. According to the predefined stopping rule, after an average follow-up of 5.6 years of treatment, the increased risk of invasive breast cancer and cardiovascular events exceeded the specified benefits included in the "global index." The absolute excess risk of events included in the "global index" was 19 per 10,000 women-years.

For those outcomes included in the WHI "global index" that reached statistical significance after 5.6 years of follow-up, the absolute excess risks per 10,000 women-years in the group treated with CE plus MPA were 7 more CHD events, 8 more strokes, 10 more PEs, and 8 more invasive breast cancers, while the absolute risk reductions per 10,000 women-years were 6 fewer colorectal cancers and 5 fewer hip fractures.

Results of the estrogen plus progestin substudy, which included 16,608 women (average 63 years of age, range 50 to 79; 83.9% White, 6.8% Black, 5.4% Hispanic, 3.9% Other) are presented in Table 6. These results reflect centrally adjudicated data after an average follow-up of 5.6 years.

Table 6: Relative and Absolute Risk Seen in the Estrogen Plus Progestin Substudy of WHI at an Average of 5.6 Years [Adapted from numerous WHI publications. WHI publications can be viewed at www.nhlbi.nih.gov/whi.] , [Results are based on centrally adjudicated data.]
 | Relative Risk CE/MPA vs. Placebo | CE/MPA n = 8,506 | Placebo n = 8,102
Event | (95% nCI [Nominal confidence intervals unadjusted for multiple looks and multiple comparisons.]) | Absolute Risk per 10,000 Women-Years
CHD events | 1.23 (0.99–1.53) | 41 | 34
Non-fatal MI | 1.28 (1.00–1.63) | 31 | 25
CHD death | 1.10 (0.70–1.75) | 8 | 8
All Strokes | 1.31 (1.03–1.68) | 33 | 25
Ischemic stroke | 1.44 (1.09–1.90) | 26 | 18
Deep vein thrombosis [Not included in "global index."] | 1.95 (1.43–2.67) | 26 | 13
Pulmonary embolism | 2.13 (1.45–3.11) | 18 | 8
Invasive breast cancer [Includes metastatic and non-metastatic breast cancer, with the exception of in situ cancer.] | 1.24 (1.01–1.54) | 41 | 33
Colorectal cancer | 0.61 (0.42–0.87) | 10 | 16
Endometrial cancer | 0.81 (0.48–1.36) | 6 | 7
Cervical cancer | 1.44 (0.47–4.42) | 2 | 1
Hip fracture | 0.67 (0.47–0.96) | 11 | 16
Vertebral fractures | 0.65 (0.46–0.92) | 11 | 17
Lower arm/wrist fractures | 0.71 (0.59–0.85) | 44 | 62
Total fractures | 0.76 (0.69–0.83) | 152 | 199
Overall Mortality [All deaths, except from breast or colorectal cancer, definite or probable CHD, PE or cerebrovascular disease.] | 1.00 (0.83–1.19) | 52 | 52
Global Index [A subset of the events was combined in a "global index" defined as the earliest occurrence of CHD events, invasive breast cancer, stroke, pulmonary embolism, colorectal cancer, hip fracture, or death due to other causes.] | 1.13 (1.02–1.25) | 184 | 165

Timing of the initiation of estrogen therapy relative to the start of menopause may affect the overall risk benefit profile. The WHI estrogen plus progestin substudy stratified by age showed in women 50–59 years of age, a non-significant trend toward reduced risk for overall mortality [HR 0.69 (95% CI 0.44–1.07)].

14.6 Women's Health Initiative Memory Study

The WHIMS estrogen-alone ancillary study of WHI enrolled 2,947 predominantly healthy hysterectomized postmenopausal women 65 to 79 years of age (45% were 65 to 69 years of age; 36% were 70 to 74 years of age; 19% were 75 years of age and older) to evaluate the effects of daily CE (0.625 mg)- alone on the incidence of probable dementia (primary outcome) compared to placebo.

After an average follow-up of 5.2 years, the relative risk of probable dementia for CE-alone versus placebo was 1.49 (95% CI 0.83–2.66). The absolute risk of probable dementia for CE-alone versus placebo was 37 versus 25 cases per 10,000 women-years. Probable dementia as defined in this study included Alzheimer's disease (AD), vascular dementia (VaD) and mixed types (having features of both AD and VaD). The most common classification of probable dementia in the treatment group and the placebo groups was AD. Since the ancillary study was conducted in women 65 to 79 years of age, it is unknown whether these findings apply to younger postmenopausal women [see Warnings and Precautions (5.3), and Use in Specific Populations (8.5)].

The WHIMS estrogen plus progestin ancillary study enrolled 4,532 predominantly healthy postmenopausal women 65 years of age and older (47% were 65 to 69 years of age; 35% were 70 to 74 years; 18% were 75 years of age and older) to evaluate the effects of daily CE (0.625 mg) plus MPA (2.5 mg) on the incidence of probable dementia (primary outcome) compared to placebo.

After an average follow-up of 4 years, the relative risk of probable dementia for CE plus MPA was 2.05 (95% CI, 1.21–3.48). The absolute risk of probable dementia for CE (0.625 mg) plus MPA (2.5 mg) versus placebo was 45 versus 22 per 10,000 women-years. Probable dementia as defined in this study included AD, VaD and mixed types (having features of both AD and VaD). The most common classification of probable dementia in both the treatment and placebo groups was AD. Since the ancillary study was conducted in women 65 to 79 years of age, it is unknown whether these findings apply to younger postmenopausal women [see Warnings and Precautions (5.3), and Use in Specific Populations (8.5)].

When data from the two populations were pooled as planned in the WHIMS protocol, the reported overall relative risk for probable dementia was 1.76 (95% CI 1.19–2.60). Differences between groups became apparent in the first year of treatment. It is unknown whether these findings apply to younger postmenopausal women [see Warnings and Precautions (5.3), and Use in Specific Populations (8.5)].

15 REFERENCES

1 Rossouw JE, et al. Postmenopausal Hormone Therapy and Risk of Cardiovascular Disease by Age and Years Since Menopause. JAMA. 2007;297:1465–1477.
2 Hsia J, et al. Conjugated Equine Estrogens and Coronary Heart Disease. Arch Int Med. 2006;166:357–365.
3 Curb JD, et al. Venous Thrombosis and Conjugated Equine Estrogen in Women Without a Uterus. Arch Int Med. 2006;166:772–780.
4 Cushman M, et al. Estrogen Plus Progestin and Risk of Venous Thrombosis. JAMA. 2004;292:1573–1580.
5 Stefanick ML, et al. Effects of Conjugated Equine Estrogens on Breast Cancer and Mammography Screening in Postmenopausal Women With Hysterectomy. JAMA. 2006;295:1647–1657.
6 Chlebowski RT, et al. Influence of Estrogen Plus Progestin on Breast Cancer and Mammography in Healthy Postmenopausal Women. JAMA. 2003;289:3234–3253.
7 Anderson GL, et al. Effects of Estrogen Plus Progestin on Gynecologic Cancers and Associated Diagnostic Procedures. JAMA. 2003;290:1739–1748.
8 Shumaker SA, et al. Conjugated Equine Estrogens and Incidence of Probable Dementia and Mild Cognitive Impairment in Postmenopausal Women. JAMA. 2004;291:2947–2958.
9 Jackson RD, et al. Effects of Conjugated Equine Estrogen on Risk of Fractures and BMD in Postmenopausal Women With Hysterectomy: Results From the Women's Health Initiative Randomized Trial. J Bone Miner Res. 2006;21:817–828.
10 Hendrix SL, et al. Effects of Conjugated Equine Estrogen on Stroke in the Women's Health Initiative. Circulation. 2006;113:2425–2434.

16 HOW SUPPLIED/STORAGE AND HANDLING

16.1 How Supplied

PREMARIN® (conjugated estrogens tablets, USP)

- Each oval green tablet contains 0.3 mg, in bottles of 100 (NDC 0046-1100-81) and 1,000 (NDC 0046-1100-91).
- Each oval blue tablet contains 0.45 mg, in bottles of 100 (NDC 0046-1101-81).
- Each oval maroon tablet contains 0.625 mg, in bottles of 100 (NDC 0046-1102-81) and 1,000 (NDC 0046-1102-91).
- Each oval white tablet contains 0.9 mg, in bottles of 100 (NDC 0046-1103-81).
- Each oval yellow tablet contains 1.25 mg, in bottles of 100 (NDC 0046-1104-81) and 1,000 (NDC 0046-1104-91).

The appearance of these tablets is a trademark of Wyeth LLC.

16.2 Storage and Handling

Store at 20° to 25°C (68° to 77°F); excursions permitted to 15° to 30°C (59° to 86°F) [see USP Controlled Room Temperature].

Dispense in a well-closed container, as defined in the USP.

17 PATIENT COUNSELING INFORMATION

Advise the patients to read the FDA-approved patient labeling (Patient Information).

17.1 Vaginal Bleeding

Inform postmenopausal women of the importance of reporting vaginal bleeding to their healthcare provider as soon as possible [see Warnings and Precautions (5.2)].

17.2 Possible Serious Adverse Reactions with Estrogens

Inform postmenopausal women of possible serious adverse reactions of estrogen therapy including Cardiovascular Disorders, Malignant Neoplasms, and Probable Dementia [see Warnings and Precautions (5.1, 5.2, 5.3)].

17.3 Possible Less Serious but Common Adverse Reactions with Estrogens

Inform postmenopausal women of possible less serious but common adverse reactions of estrogen therapy such as headache, breast pain and tenderness, nausea and vomiting.

This product’s labeling may have been updated. For the most recent prescribing information, please visit www.pfizer.com.

LAB-0467-9.0

PATIENT INFORMATION

PREMARIN®(prem-uh-rin)

(Conjugated estrogen tablets)

Read this PATIENT INFORMATION before you start taking PREMARIN and read what you get each time you refill your PREMARIN prescription. There may be new information. This information does not take the place of talking to your healthcare provider about your medical condition or your treatment.

WHAT IS THE MOST IMPORTANT INFORMATION I SHOULD KNOW ABOUT PREMARIN (AN ESTROGEN MIXTURE)?

- Using estrogen-alone may increase your chance of getting cancer of the uterus (womb)
  Report any unusual vaginal bleeding right away while you are using PREMARIN. Vaginal bleeding after menopause may be a warning sign of cancer of the uterus (womb). Your healthcare provider should check any unusual vaginal bleeding to find the cause.
- Do not use estrogen-alone to prevent heart disease, heart attacks, or dementia (decline of brain function)
- Using estrogen-alone may increase your chances of getting strokes or blood clots
- Using estrogen-alone may increase your chance of getting dementia, based on a study of women 65 years of age or older
- Do not use estrogens with progestins to prevent heart disease, heart attacks, strokes, or dementia
- Using estrogens with progestins may increase your chances of getting heart attacks, strokes, breast cancer, or blood clots
- Using estrogens with progestins may increase your chance of getting dementia, based on a study of women 65 years of age or older
- You and your healthcare provider should talk regularly about whether you still need treatment with PREMARIN

What is PREMARIN?

PREMARIN is a medicine that contains a mixture of estrogen hormones.

What is PREMARIN used for?

PREMARIN is used after menopause to:

- Reduce moderate to severe hot flushes
  Estrogens are hormones made by a woman's ovaries. The ovaries normally stop making estrogens when a woman is between 45 and 55 years old. This drop in body estrogen levels causes the "change of life" or menopause (the end of monthly menstrual periods). Sometimes, both ovaries are removed during an operation before natural menopause takes place. The sudden drop in estrogen levels causes "surgical menopause."
  When the estrogen levels begin dropping, some women get very uncomfortable symptoms, such as feelings of warmth in the face, neck, and chest, or sudden strong feelings of heat and sweating ("hot flushes"). In some women the symptoms are mild, and they will not need to take estrogens. In other women, symptoms can be more severe.
- Treat menopausal changes in and around the vagina
  You and your healthcare provider should talk regularly about whether you still need treatment with PREMARIN to control these problems. If you use PREMARIN only to treat your menopausal changes in and around your vagina, talk with your healthcare provider about whether a topical vaginal product would be better for you.
- Help reduce your chances of getting osteoporosis (thin weak bones)
  Osteoporosis from menopause is a thinning of the bones that makes them weaker and easier to break. If you use PREMARIN only to prevent osteoporosis due to menopause, talk with your healthcare provider about whether a different treatment or medicine without estrogens might be better for you.
  Weight-bearing exercise, like walking or running, and taking calcium (1500 mg/day of elemental calcium) and vitamin D (400–800 IU/day) supplements may also lower your chances of getting postmenopausal osteoporosis. It is important to talk about exercise and supplements with your healthcare provider before starting them.
  You and your healthcare provider should talk regularly about whether you still need treatment with PREMARIN.

PREMARIN is also used to:

- Treat certain conditions in women before menopause if their ovaries do not make enough estrogen naturally.
- Ease symptoms of certain cancers that have spread through the body, in men and women

Who should not take PREMARIN?

Do not take PREMARIN if you:

- Have unusual vaginal bleeding
- Currently have or have had certain cancers
  Estrogens may increase the chance of getting certain types of cancers, including cancer of the breast or uterus. If you have or have had cancer, talk with your healthcare provider about whether you should use PREMARIN.
- Had a stroke or heart attack
- Currently have or have had blood clots
- Currently have or have had liver problems
- Have been diagnosed with a bleeding disorder
- Are allergic to PREMARIN or any of its ingredients
  See the end of this leaflet for a list of ingredients in PREMARIN.

Tell your healthcare provider

- If you have any unusual vaginal bleeding
  Vaginal bleeding after menopause may be a warning sign of cancer of the uterus (womb). Your healthcare provider should check any unusual vaginal bleeding to find out the cause.
- About all of your medical problems
  Your healthcare provider may need to check you more carefully if you have certain conditions, such as asthma (wheezing), epilepsy (seizures), diabetes, migraine, endometriosis, lupus, problems with your heart, liver, thyroid, kidneys, or have high calcium levels in your blood.
- About all the medicines you take
  This includes prescription and nonprescription medicines, vitamins, and herbal supplements. Some medicines may affect how PREMARIN works. PREMARIN may also affect how your other medicines work.
- If you are going to have surgery or will be on bedrest
  You may need to stop taking PREMARIN.
- If you are pregnant or think you may be pregnant
  PREMARIN is not for pregnant women.
- If you are breastfeeding
  The hormones in PREMARIN can pass into your breast milk.

How should I take PREMARIN?

- Take one PREMARIN tablet at the same time each day
- If you miss a dose, take it as soon as possible. If it is almost time for your next dose, skip the missed dose and go back to your normal schedule. Do not take 2 doses at the same time.
- Estrogens should be used at the lowest dose possible for your treatment only as long as needed. You and your healthcare provider should talk regularly (for example, every 3 to 6 months) about the dose you are taking and whether you still need treatment with PREMARIN.
- If you see something that resembles a tablet in your stool, talk to your healthcare provider.
- Take PREMARIN with or without food.

What are the possible side effects of PREMARIN?

Side effects are grouped by how serious they are and how often they happen when you are treated.

Serious, but less common side effects include:

- Heart attack
- Stroke
- Blood clots
- Breast cancer
- Cancer of the lining of the uterus (womb)
- Cancer of the ovary
- Dementia
- High or low blood calcium
- Gallbladder disease
- Visual abnormalities
- High blood pressure
- High levels of fat (triglycerides) in your blood
- Liver problems
- Changes in your thyroid hormone levels
- Fluid retention
- Cancer changes of endometriosis
- Enlargement of benign tumors of the uterus ("fibroids")
- Severe allergic reactions
- Changes in certain laboratory test results, such as high blood sugar

Call your healthcare provider right away if you get any of the following warning signs or any other unusual symptoms that concern you:

- New breast lumps
- Unusual vaginal bleeding
- Changes in vision or speech
- Sudden new severe headaches
- Severe pains in your chest or legs with or without shortness of breath, weakness and fatigue
- Swelling of the face, lips, and tongue with or without red itchy bumps

Common side effects of PREMARIN include:

- Headache
- Breast pain
- Irregular vaginal bleeding or spotting
- Stomach/abdominal cramps/bloating
- Nausea and vomiting
- Hair loss
- Fluid retention
- Vaginal yeast infection

These are not all the possible side effects of PREMARIN. For more information, ask your healthcare provider or pharmacist for advice about side effects. You may report side effects to FDA at 1-800-FDA-1088.

What can I do to lower my chances of getting a serious side effect with PREMARIN?

- Talk with your healthcare provider regularly about whether you should continue taking PREMARIN
- If you have a uterus, talk to your healthcare provider about whether the addition of a progestin is right for you. The addition of a progestin is generally recommended for women with a uterus to reduce the chance of getting cancer of the uterus (womb).
- See your health care provider right away if you get vaginal bleeding while taking PREMARIN
- Have a pelvic exam, breast exam and mammogram (breast X-ray) every year unless your healthcare provider tells you something else. If members of your family have had breast cancer or if you have ever had breast lumps or an abnormal mammogram, you may need to have breast exams more often.
- If you have high blood pressure, high cholesterol (fat in the blood), diabetes, are overweight, or if you use tobacco, you may have higher chances for getting heart disease. Ask your healthcare provider for ways to lower your chances of getting heart disease.

General information about the safe and effective use of PREMARIN

Medicines are sometimes prescribed for conditions that are not mentioned in patient information leaflets. Do not take PREMARIN for conditions for which it was not prescribed. Do not give PREMARIN to other people, even if they have the same symptoms you have. It may harm them.

Keep PREMARIN out of the reach of children

This leaflet provides a summary of the most important information about PREMARIN. If you would like more information, talk with your healthcare provider or pharmacist.

What are the ingredients in PREMARIN?

PREMARIN contains a mixture of conjugated estrogens, which are a mixture of sodium estrone sulfate and sodium equilin sulfate and other components including sodium sulfate conjugates, 17 α-dihydroequilin, 17 α-estradiol, and 17 β-dihydroequilin.

PREMARIN 0.3 mg, 0.45 mg, 0.625 mg, 0.9 mg, and 1.25 mg tablets also contain the following inactive ingredients: calcium phosphate tribasic, hydroxypropyl cellulose, microcrystalline cellulose, powdered cellulose, hypromellose, lactose monohydrate, magnesium stearate, polyethylene glycol, sucrose and titanium dioxide.

The tablets come in different strengths and each strength tablet is a different color. The color ingredients are:

- 0.3 mg tablet (green color): D&C Yellow No. 10 and FD&C Blue No. 2.
- 0.45 mg tablet (blue color): FD&C Blue No. 2.
- 0.625 mg tablet (maroon color): FD&C Blue No. 2 and FD&C Red No. 40.
- 0.9 mg tablet (white color): D&C Red No. 30 and D&C Red No. 7.
- 1.25 mg tablet (yellow color): black iron oxide, D&C Yellow No. 10, and FD&C Yellow No. 6.

The appearance of these tablets is a trademark of Wyeth LLC.

Store at Controlled Room Temperature 20° – 25°C (68° – 77°F).

This product's labeling may have been updated. For the most recent prescribing information, please visit www.pfizer.com.

LAB-0515-7.0

Revised 04/2025

PRINCIPAL DISPLAY PANEL - 0.45 mg Tablet Bottle Label

NDC 0046-1101-81
Pfizer

PREMARIN®
(conjugated estrogens
tablets, USP)

0.45 mg

100 Tablets
Rx only

PRINCIPAL DISPLAY PANEL - 0.625 mg Tablet Bottle Label

NDC 0046-1102-91
Pfizer

PREMARIN®
(conjugated estrogens
tablets, USP)

0.625 mg

Note: Dispense in child-resistant packaging.
This package not for household use.

1,000 Tablets
Rx only

PRINCIPAL DISPLAY PANEL - 0.625 mg Tablet Bottle Carton

Pfizer
NDC 0046-1102-91
Rx only

PREMARIN®
(conjugated estrogens
tablets, USP)

0.625 mg

Note: Dispense in tight (USP), child-resistant containers.
This package not for household use.

1,000 Tablets

PRINCIPAL DISPLAY PANEL - 0.625 mg Tablet Blister Card

NDC 0046-1102-52

PROFESSIONAL
SAMPLE -
NOT FOR SALE

PREMARIN® 0.625 mg
(conjugated estrogens tablets, USP)

Blister card contains five 0.625 mg tablets

Rx only

PRINCIPAL DISPLAY PANEL - 1.25 mg Tablet Bottle Label

NDC 0046-1104-91
Pfizer

PREMARIN®
(conjugated estrogens
tablets, USP)

1.25 mg

Note: Dispense in tight (USP), child-resistant containers.
This package not for household use.

1,000 Tablets
Rx only

PRINCIPAL DISPLAY PANEL - 1.25 mg Tablet Bottle Carton

NDC 0046-1104-91
Pfizer

PREMARIN®
(conjugated estrogens
tablets, USP)

1.25 mg

Note:
Dispense in tight (USP),
child-resistant containers.
This package not for household use.

1,000 Tablets
Rx only

PRINCIPAL DISPLAY PANEL - 0.3 mg Tablet Bottle Label

NDC 0046-1100-91
Pfizer

PREMARIN®
(conjugated estrogens
tablets, USP)

0.3 mg

Note: Dispense in child-resistant packaging.
This package not for household use.

1,000 Tablets
Rx only

PRINCIPAL DISPLAY PANEL - 0.3 mg Tablet Bottle Carton

Pfizer
NDC 0046-1100-91
Rx only

PREMARIN®
(conjugated estrogens
tablets, USP)

0.3 mg

Note: Dispense in tight (USP), child-resistant containers.
This package not for household use.

1,000 Tablets

PRINCIPAL DISPLAY PANEL - 0.3 mg Tablet Blister Card

NDC 0046-1100-52

PROFESSIONAL
SAMPLE -
NOT FOR SALE

PREMARIN® 0.3 mg
(conjugated estrogens tablets, USP)

Blister card contains five 0.3 mg tablets

Rx only

PRINCIPAL DISPLAY PANEL - 0.9 mg Tablet Bottle Label

NDC 0046-1103-81
Pfizer

PREMARIN®
(conjugated estrogens
tablets, USP)

0.9 mg

100 Tablets
Rx only